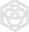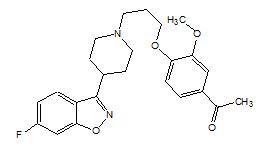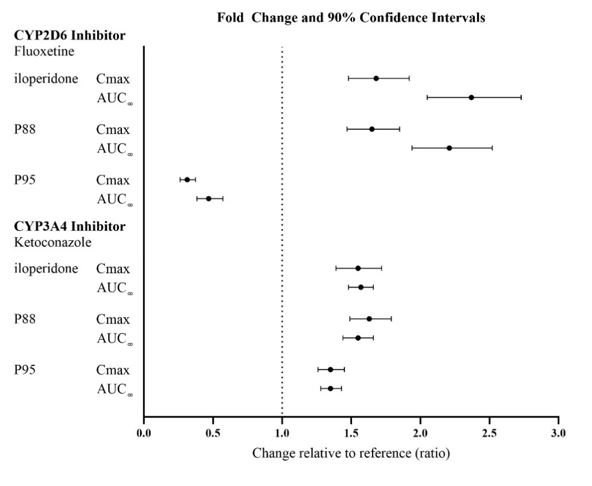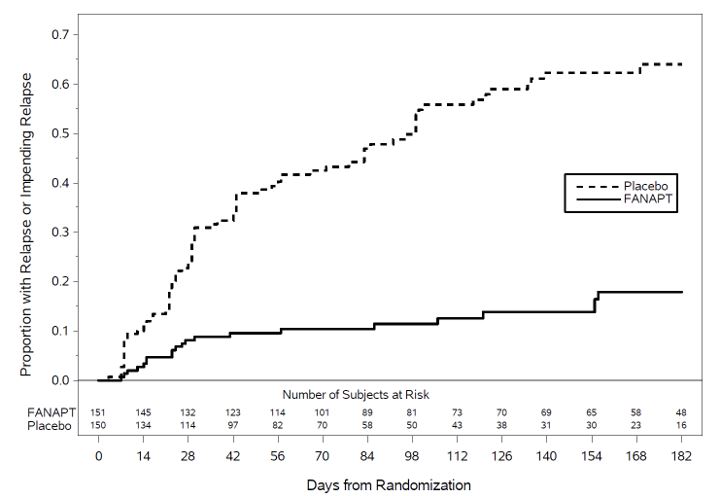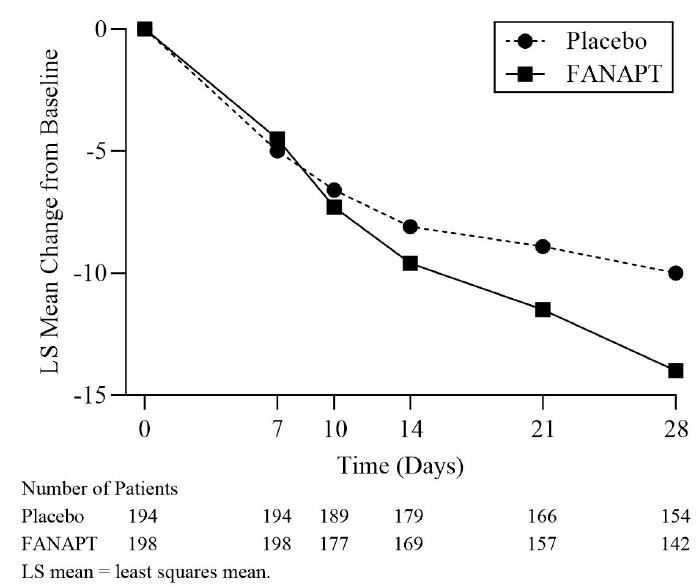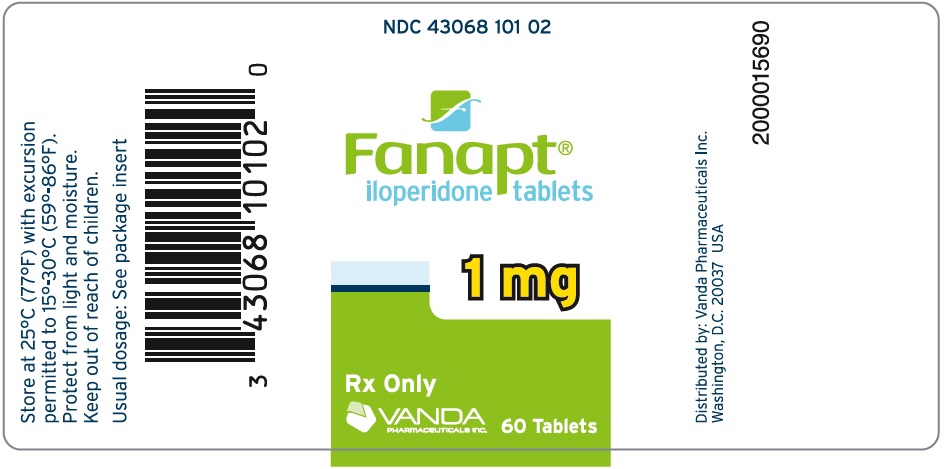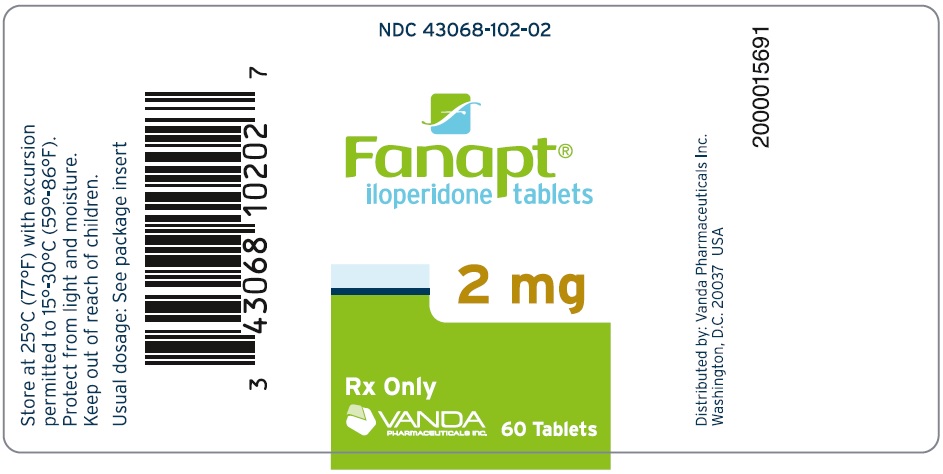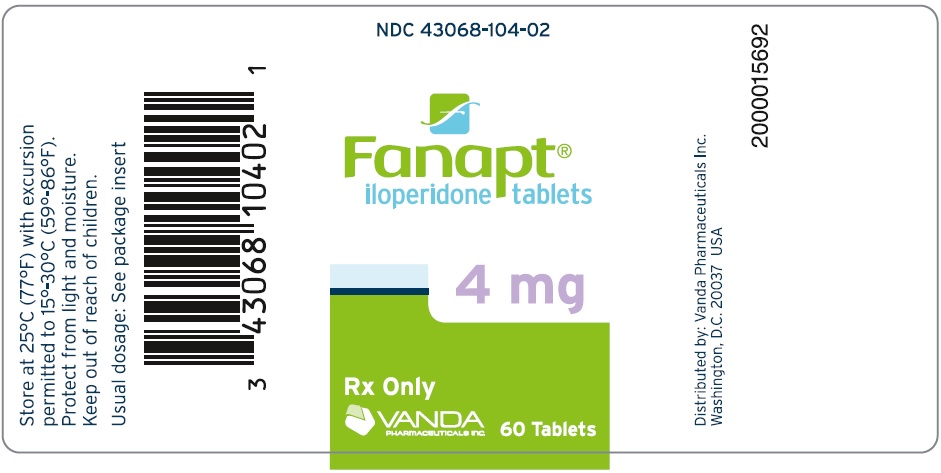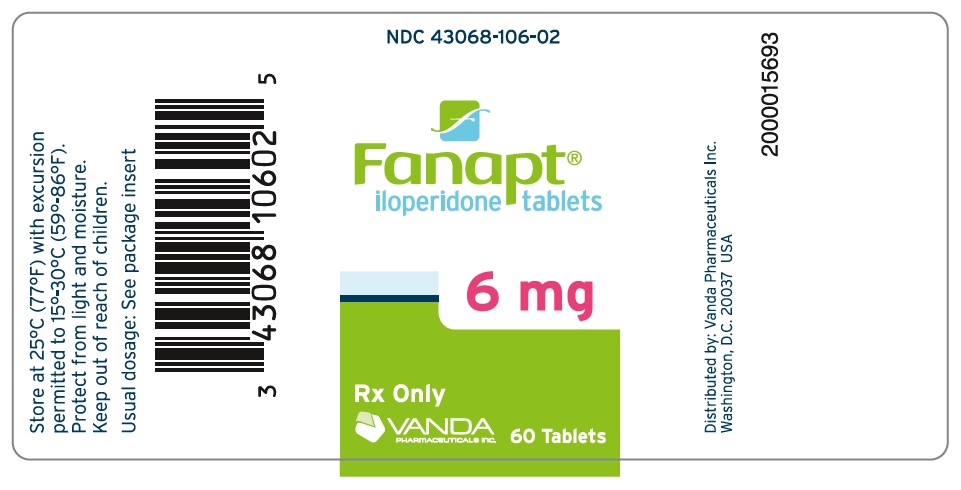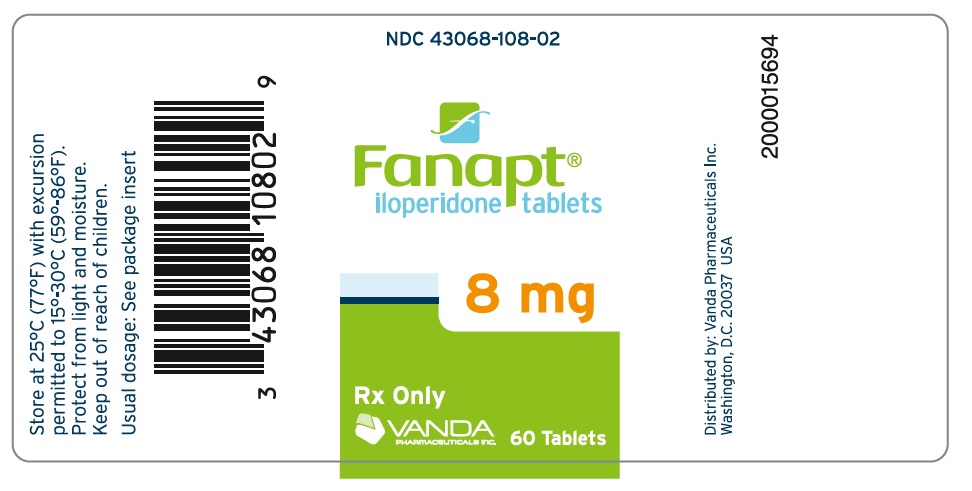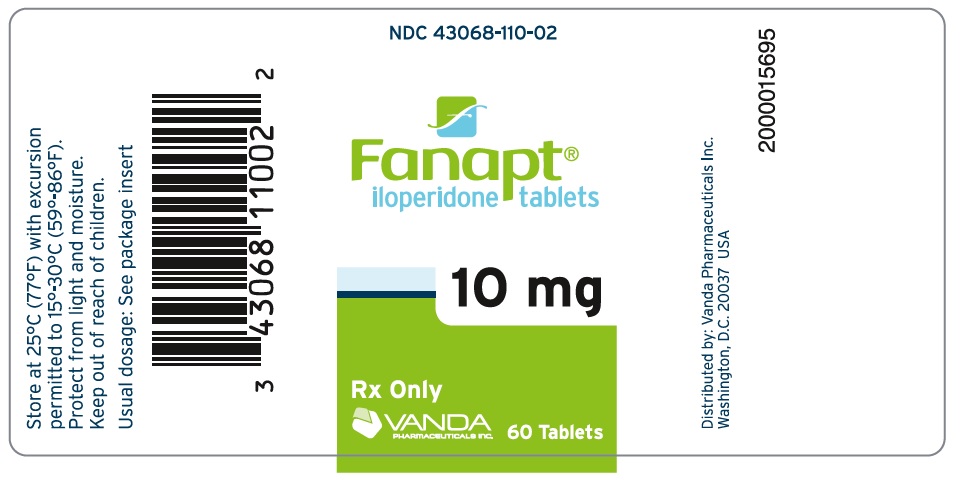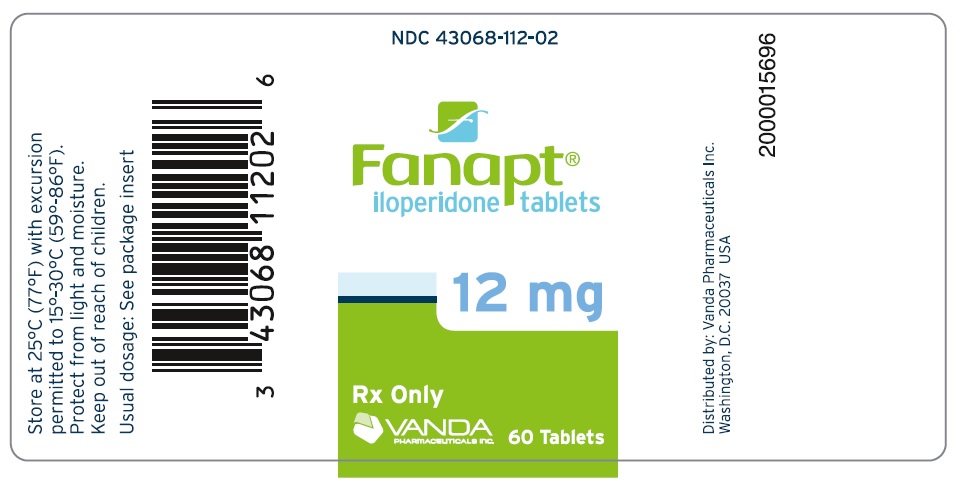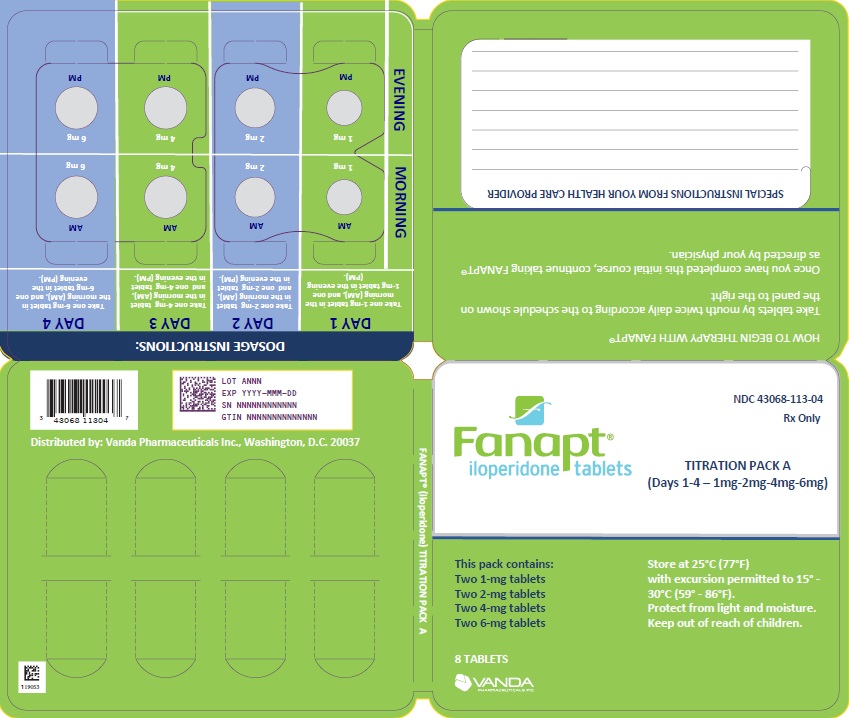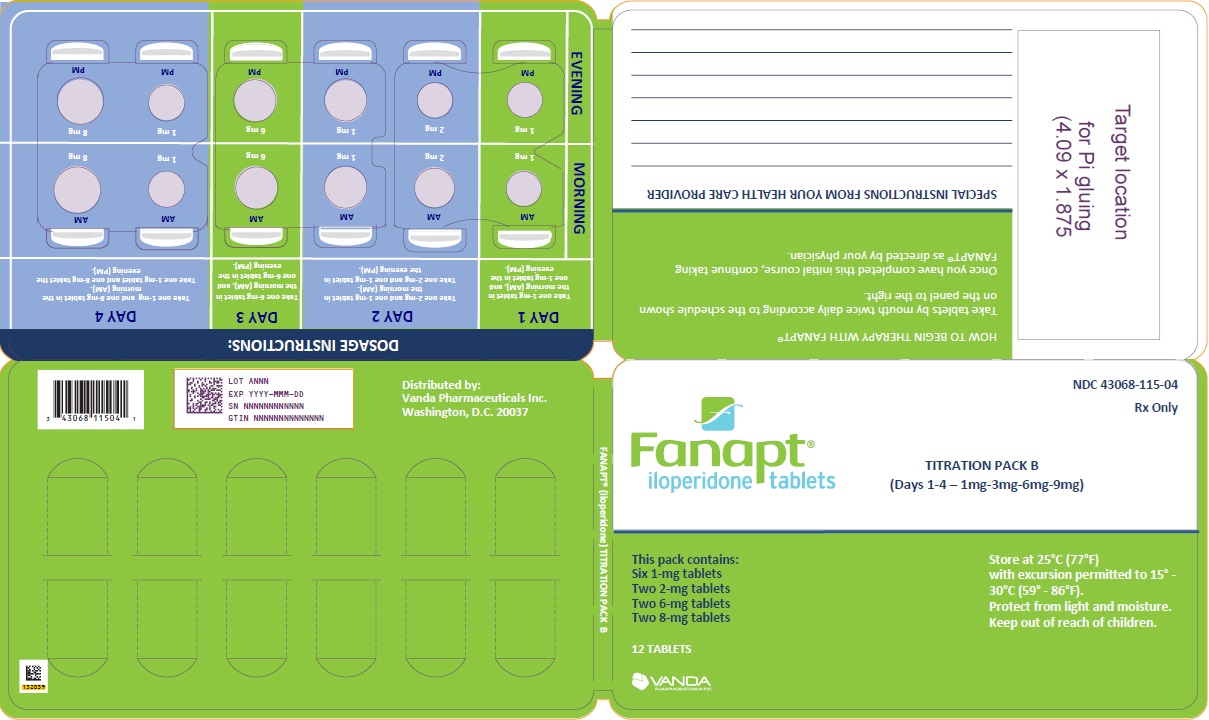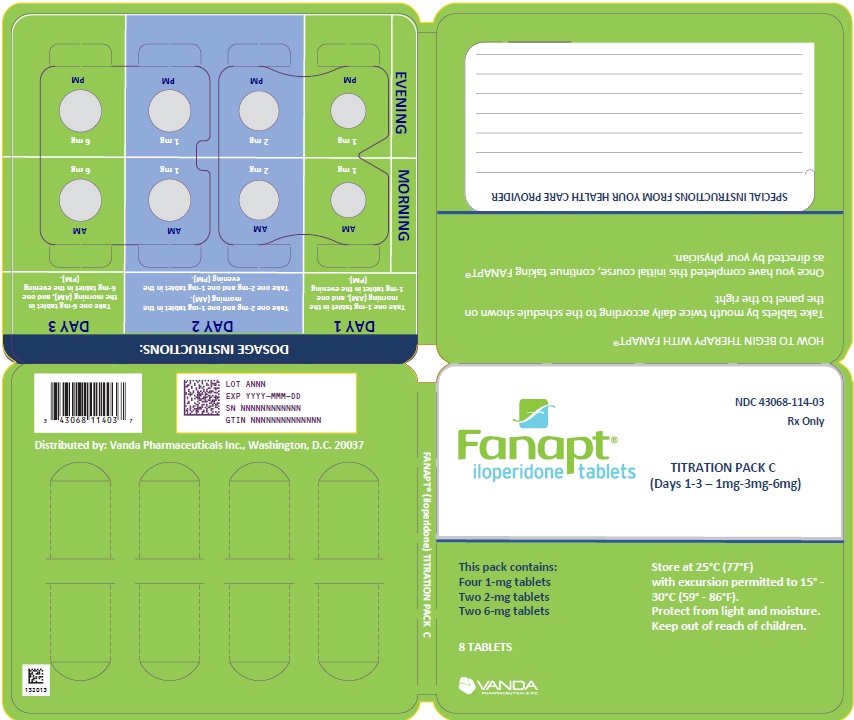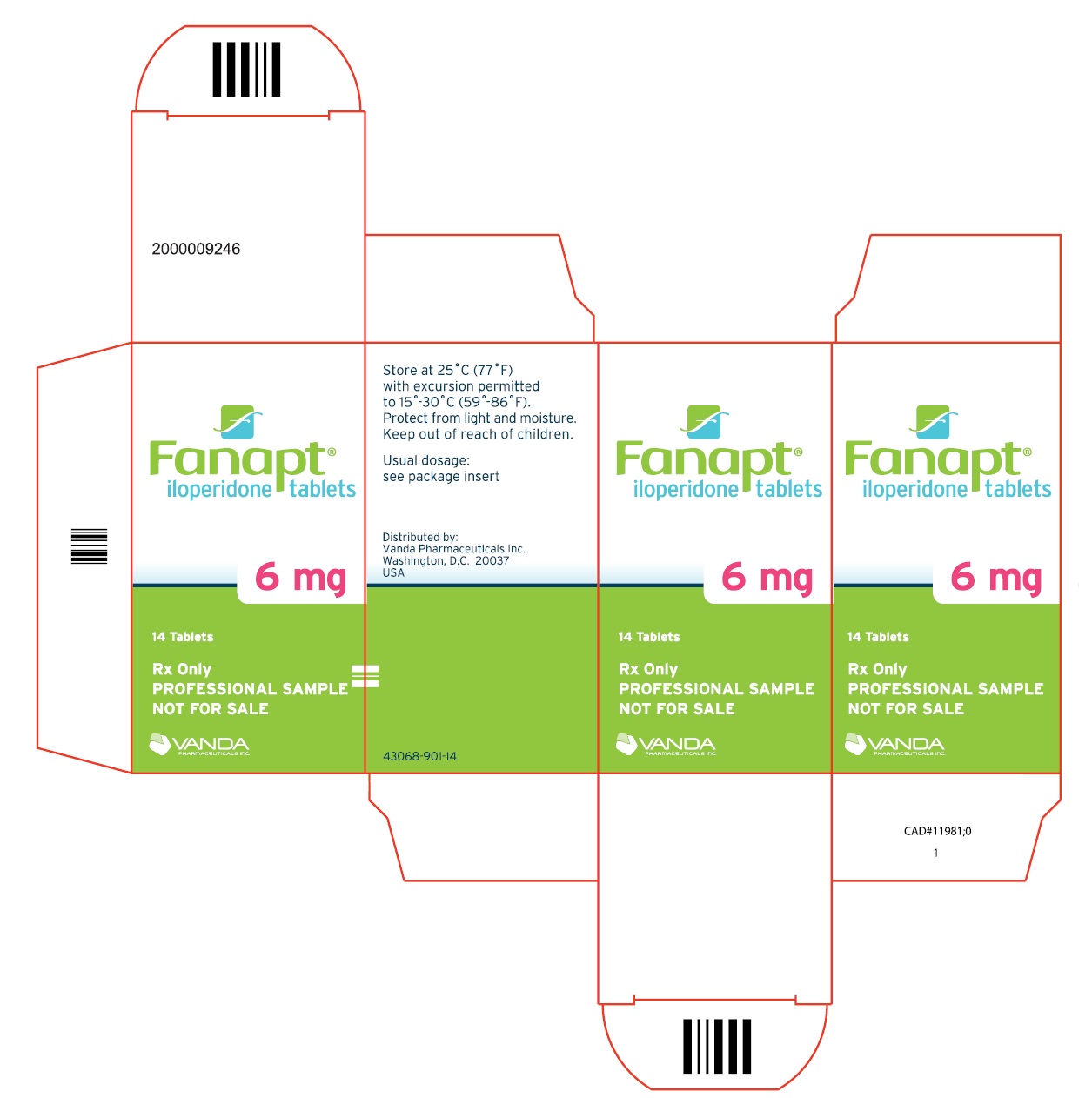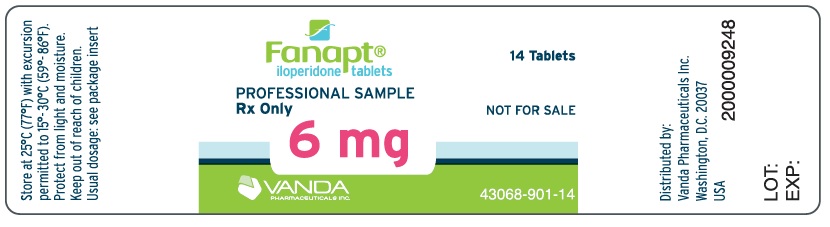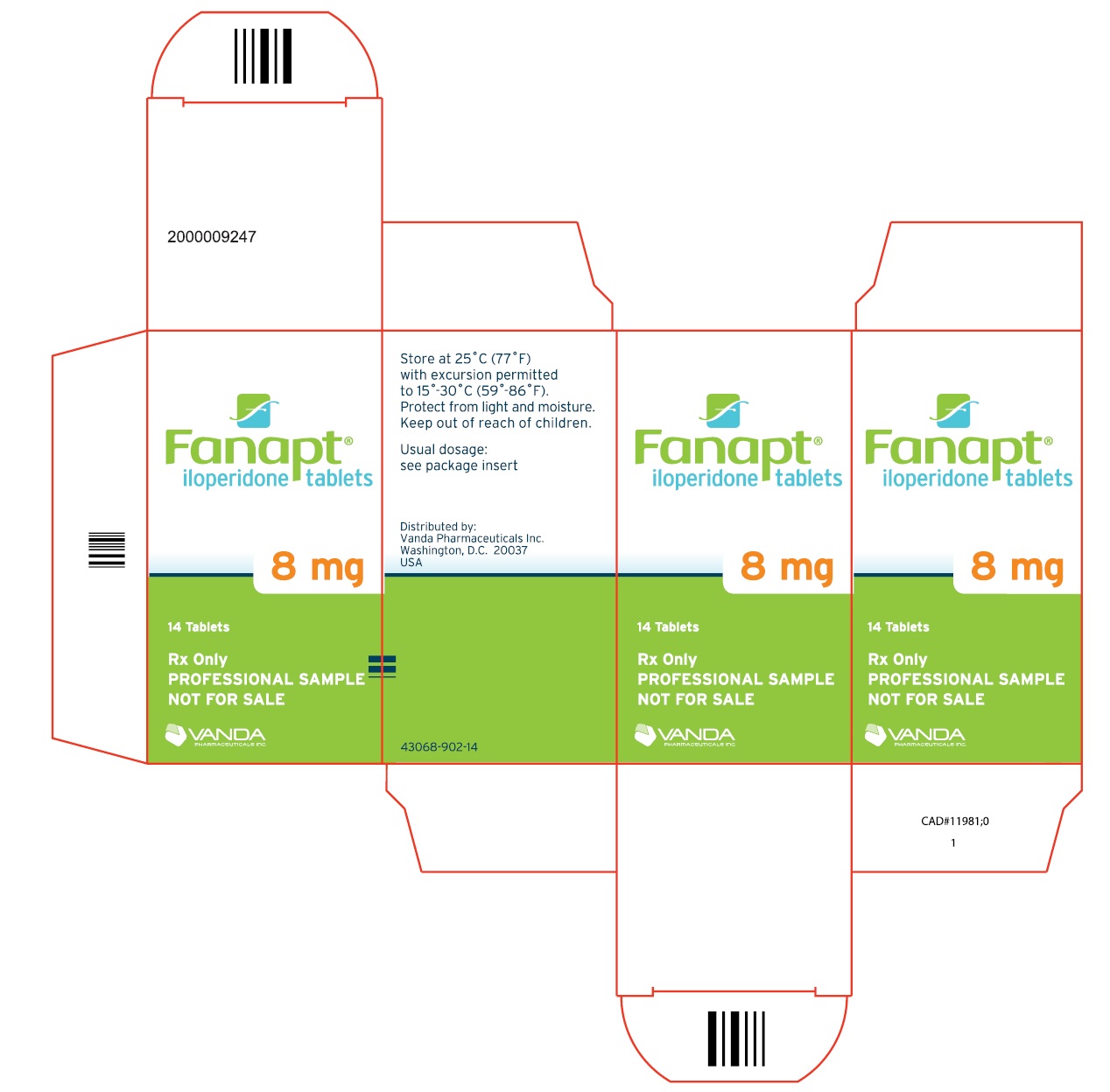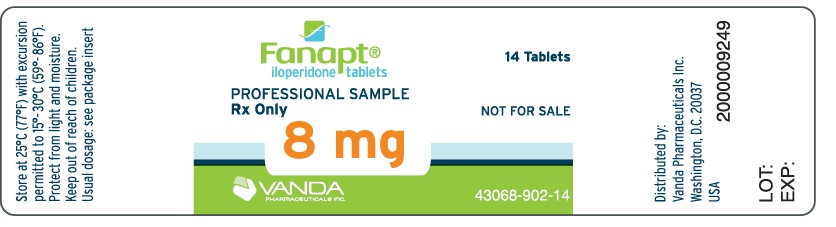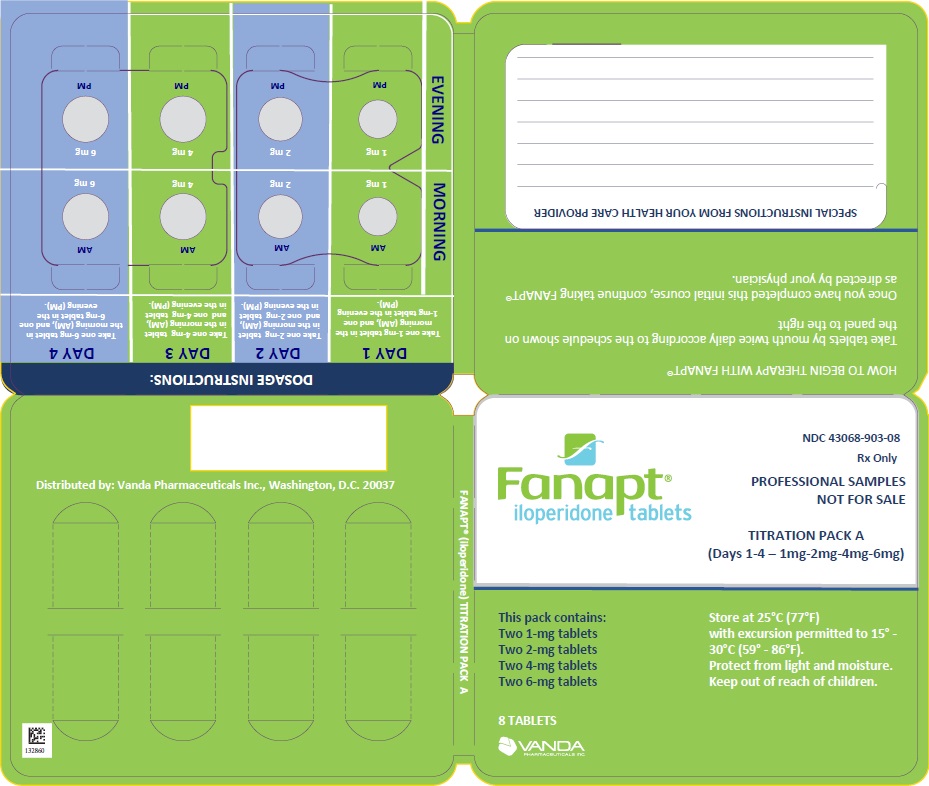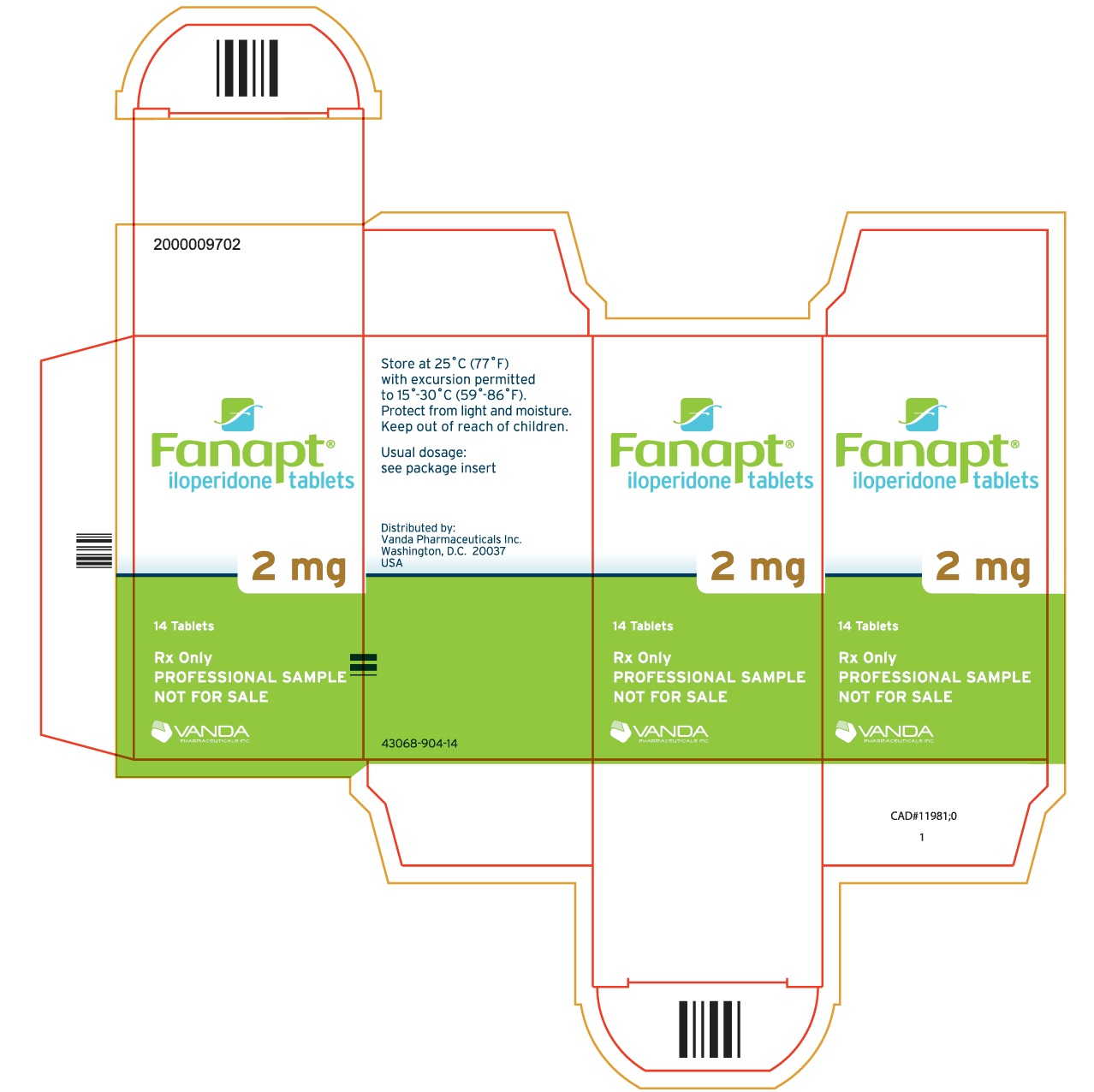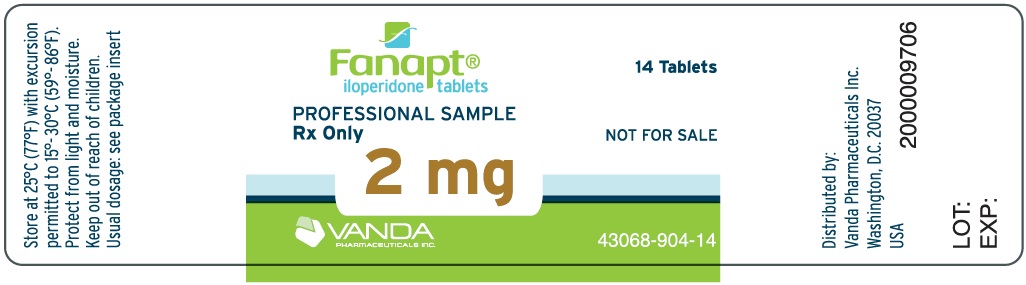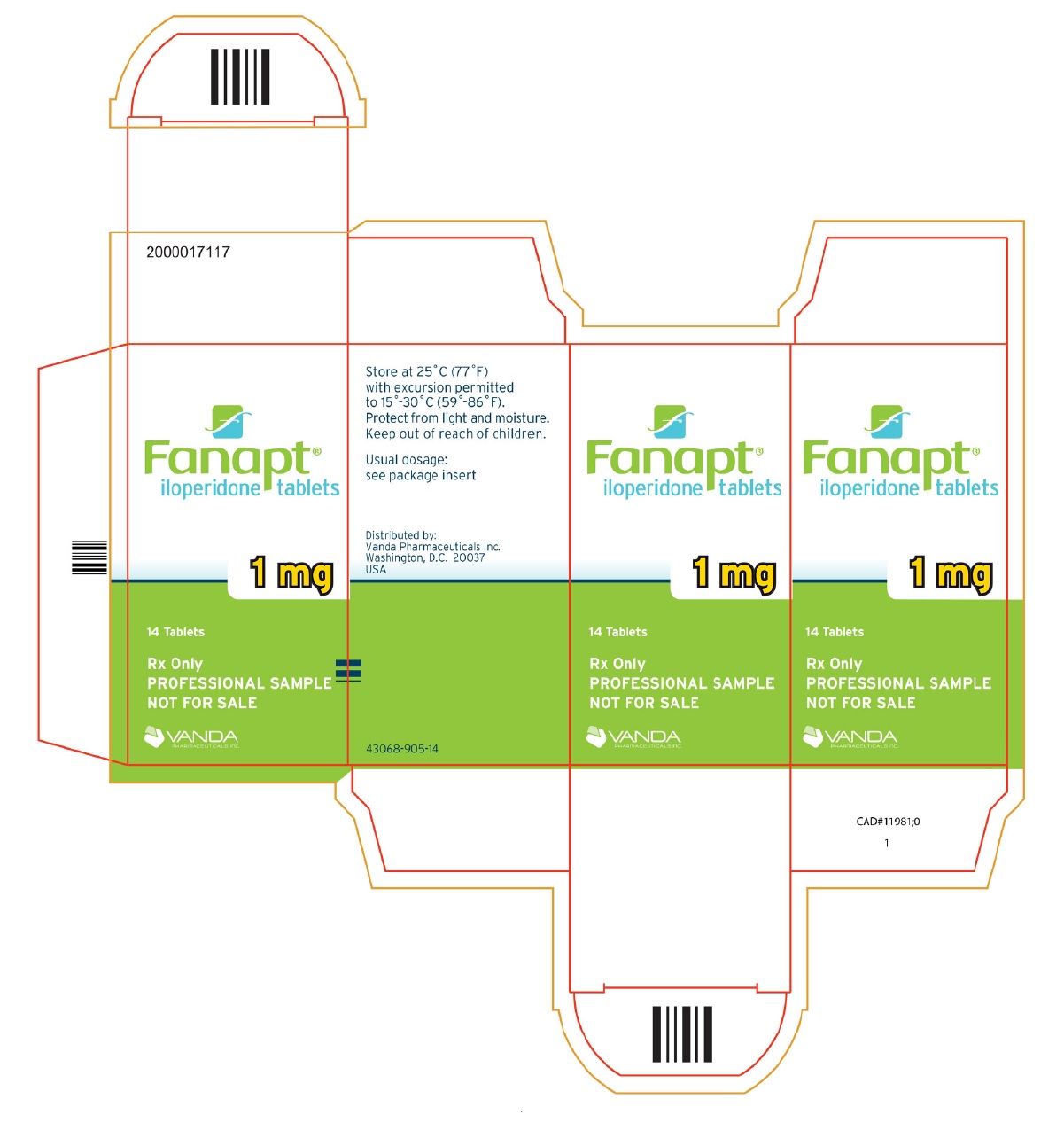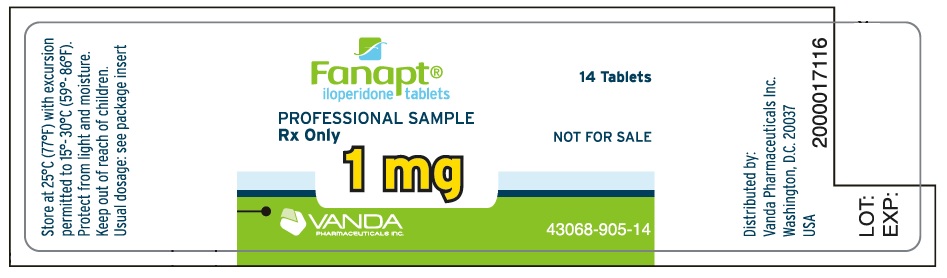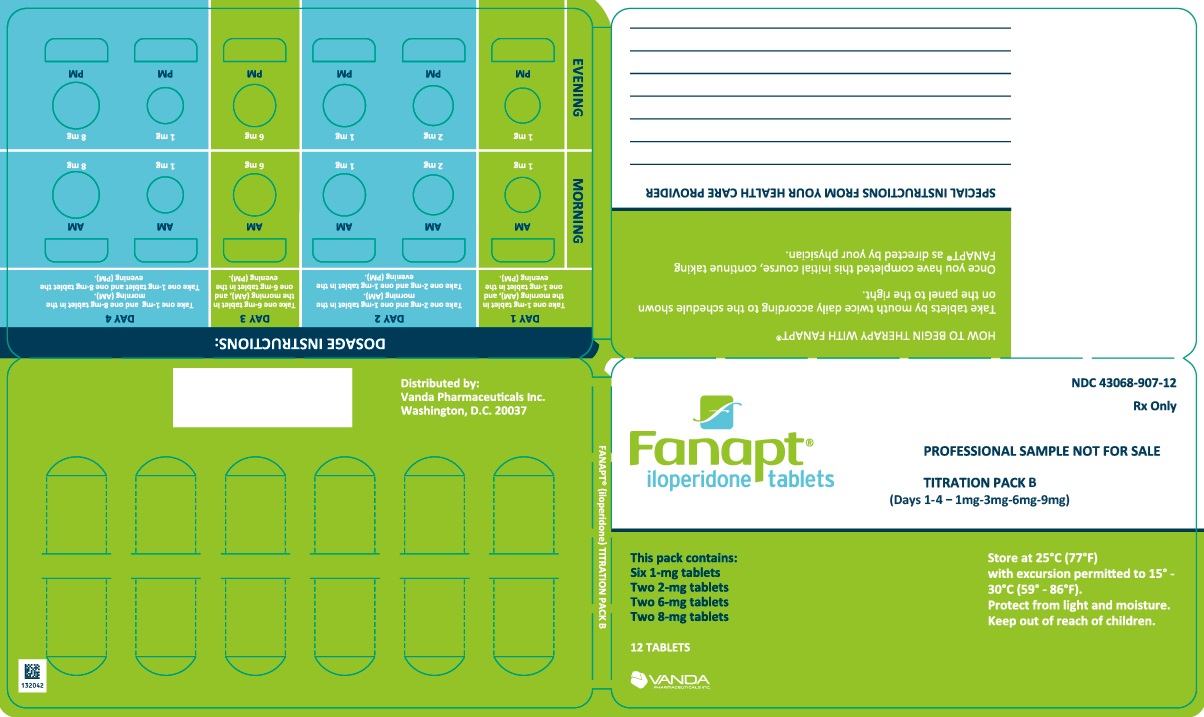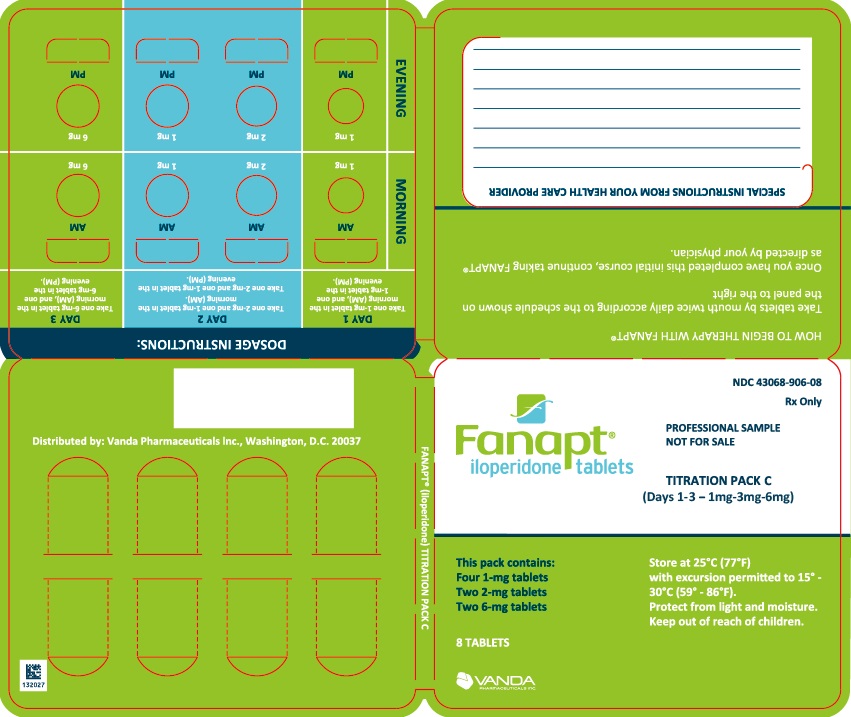 DRUG LABEL: FANAPT
NDC: 43068-101 | Form: TABLET
Manufacturer: Vanda Pharmaceuticals Inc.
Category: prescription | Type: HUMAN PRESCRIPTION DRUG LABEL
Date: 20250630

ACTIVE INGREDIENTS: ILOPERIDONE 1 mg/1 1

HIGHLIGHTS OF PRESCRIBING INFORMATION

These highlights do not include all the information needed to use FANAPT safely and effectively. See full prescribing information for FANAPT.
FANAPT® (iloperidone) tablets, for oral use
Initial U.S. Approval: 2009

RECENT MAJOR CHANGES

Indications and Usage (1) 4/2024

Dose and Administration (2.1, 2.2, 2.3, 2.4) 4/2024

Warnings and Precautions (5.6, 5.7, 5.11, 5.15, 5.16) 4/2024

Warnings and Precautions (5.11) 1/2025

Warnings and Precautions, Suicide (5.14) Removed 4/2024

WARNING: INCREASED MORTALITY IN ELDERLY PATIENTS WITH DEMENTIA-RELATED PSYCHOSIS

See full prescribing information for complete boxed warning.

Elderly patients with dementia-related psychosis treated with antipsychotic drugs are at an increased risk of death. FANAPT is not approved for use in patients with dementia-related psychosis. (5.1)

1 INDICATIONS AND USAGE

FANAPT is an atypical antipsychotic indicated for:

- Treatment of schizophrenia in adults. (1, 14.1)
- Acute treatment of manic or mixed episodes associated with bipolar I disorder in adults. (1, 14.2)

2 DOSAGE AND ADMINISTRATION

- Administer FANAPT orally twice daily without regard to meals. (2.1)
- Titrate the dosage of FANAPT to avoid orthostatic hypotension. See Full Prescribing Information for titration schedule. (2.1)
- Recommended Dosage:

Indication | Starting Dosage | Recommended Dosage
Schizophrenia (2.1) | 1 mg twice daily | 6 mg to 12 mg twice daily
Bipolar Mania (2.1) | 1 mg twice daily | 12 mg twice daily

- CYP2D6 Poor Metabolizers: See Full Prescribing Information for titration schedule and recommended dosage. (2.2)

3 DOSAGE FORMS AND STRENGTHS

1 mg, 2 mg, 4 mg, 6 mg, 8 mg, 10 mg and 12 mg tablets. (3)

4 CONTRAINDICATIONS

Known hypersensitivity to FANAPT or to any components in the formulation. (4, 6.2)

5 WARNINGS AND PRECAUTIONS

- Cerebrovascular Adverse Reactions in Elderly Patients with Dementia- Related Psychosis: Increased incidence of cerebrovascular adverse reactions (e.g., stroke, transient ischemic attack). (5.2)
- QT prolongation: Prolongs QT interval and may be associated with arrhythmia and sudden death. Avoid use of FANAPT in combination with other drugs that are known to prolong QTc; use caution and consider dose modification when prescribing FANAPT with other drugs that inhibit FANAPT metabolism. Monitor serum potassium and magnesium in patients at risk for electrolyte disturbances. (1, 5.3, 7.1, 7.2, 12.3)
- Neuroleptic Malignant Syndrome (NMS): Manage with immediate discontinuation of drug and close monitoring. (5.4)
- Tardive dyskinesia: Discontinue if clinically appropriate. (5.5)
- Metabolic Changes: Monitor for hyperglycemia/diabetes mellitus, dyslipidemia and weight gain. (5.6)
- Orthostatic hypotension and Syncope: Monitor heart rate and blood pressure and warn patients with known cardiovascular or cerebrovascular disease, and risk of dehydration or syncope. (5.7)
- Seizures: Use cautiously in patients with a history of seizures or with conditions that lower seizure threshold. (5.9)
- Leukopenia, Neutropenia, and Agranulocytosis have been reported with antipsychotics. Perform complete blood counts (CBC) in patients with pre-existing low white blood cell count (WBC) or a history of leukopenia/neutropenia. Consider discontinuing FANAPT if clinically significant decline in WBC occurs in the absence of other causative factors. (5.10)
- Priapism: Cases have been reported in association with FANAPT treatment. Severe priapism may require surgical intervention. (5.14)
- Potential for cognitive and motor impairment: Use caution when operating machinery. (5.15)
- Intraoperative Floppy Iris Syndrome (IFIS): IFIS during cataract surgery may require modifications to the surgical technique. (5.16)

6 ADVERSE REACTIONS

Commonly observed adverse reactions (incidence ≥5% and 2-fold greater than placebo) were (6.1):

- Schizophrenia: dizziness, dry mouth, fatigue, nasal congestion, orthostatic hypotension, somnolence, tachycardia, and weight increased.
- Bipolar mania: tachycardia, dizziness, dry mouth, hepatic enzymes increased, nasal congestion, weight increased, hypotension, and somnolence.

To report SUSPECTED ADVERSE REACTIONS, contact Vanda Pharmaceuticals Inc. at 1-844-GO-VANDA (1-844-468-2632) or FDA at 1-800-FDA-1088 or www.fda.gov/medwatch.

7 DRUG INTERACTIONS

The dose of FANAPT should be reduced in patients co-administered a strong CYP2D6 or CYP3A4 inhibitor. (2.2, 7.1)

8 USE IN SPECIFIC POPULATIONS

- Pregnancy: May cause extrapyramidal and/or withdrawal symptoms in neonates with third trimester exposure. (8.1)
- Lactation: Advise not to breast feed. (8.2)
- Pediatric Use: Safety and effectiveness not established in children and adolescents. (8.4)
- Hepatic Impairment: FANAPT is not recommended for patients with severe hepatic impairment. (2.3, 8.6)

FULL PRESCRIBING INFORMATION

WARNING: INCREASED MORTALITY IN ELDERLY PATIENTS WITH DEMENTIA-RELATED PSYCHOSIS

Elderly patients with dementia-related psychosis treated with antipsychotic drugs are at an increased risk of death.

FANAPT is not approved for the treatment of patients with dementia-related psychosis [see Warnings and Precautions (5.1)].

1 INDICATIONS AND USAGE

FANAPT® is indicated for:

- Treatment of schizophrenia in adults [see Clinical Studies (14.1)].
- Acute treatment of manic or mixed episodes associated with bipolar I disorder in adults [see Clinical Studies (14.2)].

2 DOSAGE AND ADMINISTRATION

2.1 Recommended Dosage

Titrate FANAPT to avoid orthostatic hypotension [see Warnings and Precautions (5.7)].

Administer FANAPT orally with or without food.

Table 1 includes dosage recommendations for FANAPT for the treatment of schizophrenia and the acute treatment of manic or mixed episodes associated with bipolar I disorder in adults.

Table 1: Dosage Recommendations for FANAPT in Adults for the Treatment of Schizophrenia or
Acute Treatment of Manic or Mixed Episodes Associated with Bipolar I Disorder

Indication and Population | Titration schedule |  |  |  |  |  |  | Recommended Dosage
Indication and Population | Day 1 | Day 2 | Day 3 | Day 4 | Day 5 | Day 6 | Day 7 | Recommended Dosage
Schizophrenia | 1mg twice daily | 2 mg twice daily | 4 mg twice daily | 6 mg twice daily | 8 mg twice daily | 10 mg twice daily | 12 mg twice daily | 6 mg to 12 mg twice daily
Bipolar I Disorder Manic or Mixed Episodes | 1 mg twice daily | 3 mg twice daily | 6 mg twice daily | 9 mg twice daily | 12 mg twice daily | Titration complete |  | 12 mg twice daily

2.2 Dosage Recommendations for Use in Patients Who Are Known CYP2D6 Poor Metabolizers

Reduce the dose of FANAPT by one-half for CYP2D6 poor metabolizers [see Clinical Pharmacology (12.3, 12.5)]. Table 2 includes dosage recommendations for FANAPT in adults who are CYP2D6 poor metabolizers.

Table 2: Dosage Recommendations for FANAPT in Adults with Schizophrenia or Bipolar I Disorder
Who are CYP2D6 Poor Metabolizers

Indication and Population | Titration schedule |  |  |  |  |  |  | Recommended Dosage
Indication and Population | Day 1 | Day 2 | Day 3 | Day 4 | Day 5 | Day 6 | Day 7 | Recommended Dosage
Schizophrenia | 1mg twice daily | 2 mg twice daily | 4 mg twice daily | 6 mg twice daily | Titration complete |  |  | 3 mg to 6 mg twice daily
Bipolar I Disorder Manic or Mixed Episodes | 1 mg twice daily | 3 mg twice daily | 6 mg twice daily | Titration complete |  |  |  | 6 mg twice daily

2.3 Dosage Recommendations in Patients with Hepatic Impairment

No dose adjustment for FANAPT is needed in patients with mild hepatic impairment. Patients with moderate hepatic impairment may require dose reduction, if clinically indicated. FANAPT is not recommended for patients with severe hepatic impairment [see Use in Specific Populations (8.6)].

2.4 Dosage Modifications for Concomitant Use with Strong CYP2D6 Inhibitors and Strong CYP3A4 Inhibitors

Coadministration with Strong CYP2D6 Inhibitors

Reduce the dose of FANAPT one-half when administered concomitantly with strong CYP2D6 inhibitors such as fluoxetine or paroxetine. When the CYP2D6 inhibitor is withdrawn from the combination therapy, increase the dose of FANAPT to where it was before [see Drug Interactions (7.1)].

Coadministration with Strong CYP3A4 Inhibitors

Reduce the dose of FANAPT by one-half when administered concomitantly with strong CYP3A4 inhibitors such as ketoconazole or clarithromycin. When the CYP3A4 inhibitor is withdrawn from the combination therapy, increase the dose of FANAPT to where it was before [see Drug Interactions (7.1)].

Coadministration with Strong CYP2D6 and Strong CYP3A4 Inhibitors

Reduce the dose of FANAPT by about one-half if administered concomitantly with inhibitors of CYP2D6 and CYP3A4. When both CYP2D6 and CYP3A4 inhibitors are withdrawn from the combination therapy, increase the dose of FANAPT to where it was before [see Drug Interactions (7.1)].

2.5 Reinitiation of Treatment in Patients Previously Discontinued

Although there are no data to specifically address reinitiation of treatment, it is recommended that the initiation titration schedule be followed whenever patients have had an interval off FANAPT of more than 3 days.

3 DOSAGE FORMS AND STRENGTHS

FANAPT tablets are available in the following strengths: 1 mg, 2 mg, 4 mg, 6 mg, 8 mg, 10 mg, and 12 mg. The tablets are white, round, flat, beveled-edged and identified with a logo “” debossed on one side and tablet strength “1”, “2”, “4”, “6”, “8”, “10”, or “12” debossed on the other side.

4 CONTRAINDICATIONS

FANAPT is contraindicated in individuals with a known hypersensitivity reaction to the product. Anaphylaxis, angioedema, and other hypersensitivity reactions have been reported [see Adverse Reactions (6.2)].

5 WARNINGS AND PRECAUTIONS

5.1 Increased Mortality in Elderly Patients with Dementia-Related Psychosis

Elderly patients with dementia-related psychosis treated with antipsychotic drugs are at an increased risk of death. Analyses of 17 dementia-related psychosis placebo-controlled trials (modal duration of 10 weeks) largely in patients taking atypical antipsychotic drugs, revealed a risk of death in the drug-treated patients of between 1.6 to 1.7 times that in placebo-treated patients. Over the course of a typical 10-week controlled trial, the rate of death in drug-treated patients was about 4.5%, compared to a rate of about 2.6% in placebo-treated patients.

Although the causes of death were varied, most of the deaths appeared to be either cardiovascular (e.g., heart failure, sudden death) or infectious (e.g., pneumonia) in nature. FANAPT is not approved for the treatment of patients with dementia-related psychosis [see Boxed Warning, Warnings and Precautions (5.2)].

5.2 Cerebrovascular Adverse Reactions, Including Stroke, in Elderly Patients with Dementia-Related Psychosis

In placebo-controlled trials in elderly subjects with dementia, patients randomized to risperidone, aripiprazole, and olanzapine had a higher incidence of stroke and transient ischemic attack, including fatal stroke. FANAPT is not approved for the treatment of patients with dementia-related psychosis [see Boxed Warning, Warnings and Precautions (5.1)].

5.3 QT Prolongation

In an open-label QTc study in patients with schizophrenia or schizoaffective disorder (n=160), FANAPT was associated with QTc prolongation of 9 msec at an iloperidone dose of 12 mg twice daily. The effect of FANAPT on the QT interval was augmented by the presence of CYP450 2D6 or 3A4 metabolic inhibition (paroxetine 20 mg once daily and ketoconazole 200 mg twice daily, respectively). Under conditions of metabolic inhibition for both 2D6 and 3A4, FANAPT 12 mg twice daily was associated with a mean QTcF increase from baseline of about 19 msec.

No cases of torsade de pointes or other severe cardiac arrhythmias were observed during the pre-marketing clinical program.

The use of FANAPT should be avoided in combination with other drugs that are known to prolong QTc including Class 1A (e.g., quinidine, procainamide) or Class III (e.g., amiodarone, sotalol) antiarrhythmic medications, antipsychotic medications (e.g., chlorpromazine, thioridazine), antibiotics (e.g., gatifloxacin, moxifloxacin), or any other class of medications known to prolong the QTc interval (e.g., pentamidine, levomethadyl acetate, methadone). FANAPT should also be avoided in patients with a known genetic susceptibility to congenital long QT syndrome and in patients with a history of cardiac arrhythmias.

Certain circumstances may increase the risk of torsade de pointes and/or sudden death in association with the use of drugs that prolong the QTc interval, including (1) bradycardia; (2) hypokalemia or hypomagnesemia; (3) concomitant use of other drugs that prolong the QTc interval; and (4) presence of congenital prolongation of the QT interval; (5) recent acute myocardial infarction; and/or (6) uncompensated heart failure.

Caution is warranted when prescribing FANAPT with drugs that inhibit FANAPT metabolism [see Drug Interactions (7.1)], and in patients with reduced activity of CYP2D6 [see Clinical Pharmacology (12.3, 12.5)].

It is recommended that patients being considered for FANAPT treatment who are at risk for significant electrolyte disturbances have baseline serum potassium and magnesium measurements with periodic monitoring. Hypokalemia (and/or hypomagnesemia) may increase the risk of QT prolongation and arrhythmia. FANAPT should be avoided in patients with histories of significant cardiovascular illness, e.g., QT prolongation, recent acute myocardial infarction, uncompensated heart failure, or cardiac arrhythmia. FANAPT should be discontinued in patients who are found to have persistent QTc measurements >500 msec.

If patients taking FANAPT experience symptoms that could indicate the occurrence of cardiac arrhythmias, e.g., dizziness, palpitations, or syncope, the prescriber should initiate further evaluation, including cardiac monitoring.

5.4 Neuroleptic Malignant Syndrome (NMS)

Neuroleptic Malignant Syndrome (NMS), a potentially fatal symptom complex, has been reported in association with administration of antipsychotic drugs, including FANAPT. Clinical manifestations include hyperpyrexia, muscle rigidity, altered mental status (including catatonic signs), and evidence of autonomic instability (irregular pulse or blood pressure, tachycardia, diaphoresis, and cardiac dysrhythmia). Additional signs may include elevated creatine phosphokinase, myoglobinuria (rhabdomyolysis), and acute renal failure.

If NMS is suspected, immediately discontinue FANAPT and provide intensive symptomatic treatment and monitoring.

5.5 Tardive Dyskinesia

Tardive dyskinesia, a syndrome consisting of potentially irreversible, involuntary, dyskinetic movements, may develop in patients treated with antipsychotic drugs. The risk appears to be highest among the elderly, especially elderly women, but it is impossible to predict, which patients will develop the syndrome. Whether antipsychotic drug products differ in their potential to cause tardive dyskinesia is unknown.

The risk of developing tardive dyskinesia and the likelihood that it will become irreversible increase with the duration of treatment and cumulative dose. The syndrome can develop after relatively brief treatment periods at low doses. It may also occur after discontinuation of treatment.

Tardive dyskinesia may remit, partially or completely, if antipsychotic treatment is discontinued. Antipsychotic treatment itself may suppress (or partially suppress) the signs and symptoms of the syndrome, possibly masking the underlying process. The effect that symptomatic suppression has upon the long-term course of the syndrome is unknown.

Given these considerations, FANAPT should be prescribed in a manner that is most likely to reduce the risk of tardive dyskinesia. Chronic antipsychotic treatment should generally be reserved for patients: 1) who suffer from a chronic illness that is known to respond to antipsychotic drugs, and (2) for whom alternative, equally effective, but potentially less harmful treatments are not available or appropriate. In patients who do require chronic treatment, use the lowest dose and the shortest duration of treatment producing a satisfactory clinical response. Periodically reassess the need for continued treatment.

If signs and symptoms of tardive dyskinesia appear in a patient on FANAPT, drug discontinuation should be considered. However, some patients may require treatment with FANAPT despite the presence of the syndrome.

5.6 Metabolic Changes

Atypical antipsychotic drugs have been associated with metabolic changes that may increase cardiovascular/cerebrovascular risk. These metabolic changes include hyperglycemia, dyslipidemia, and body weight gain. While all atypical antipsychotic drugs have been shown to produce some metabolic changes, each drug in the class has its own specific risk profile.

Hyperglycemia and Diabetes Mellitus

Hyperglycemia, in some cases extreme and associated with ketoacidosis or hyperosmolar coma or death, has been reported in patients treated with atypical antipsychotics including FANAPT. Assess fasting plasma glucose before or soon after initiation of antipsychotic medication and monitor periodically during long-term treatment.

Schizophrenia

In a 4-week fixed-dose placebo-controlled study of adults with schizophrenia, the mean change from baseline in serum glucose was 6.6 mg/dL and -0.5 mg/dL for FANAPT and placebo treated patients, respectively. The proportion of patients with shifts in fasting glucose from normal (<100 mg/dL) to high (≥126 mg/dL) were 10.7% and 2.5% for FANAPT and placebo treated patients, respectively.

In pooled analyses from clinical studies, for adults with schizophrenia remaining on treatment with FANAPT 10-16 mg/day glucose increased, on average, from baseline by 1.8 mg/dL at 3-6 months (N=773) and by 5.4 mg/dL at 6-12 months (N=723) and at >12 months (N=425) of treatment. In a smaller group of patients remaining on treatment with FANAPT 20-24 mg/day, glucose decreased by 3.6 mg/dL at 3-6 months (N=34); by 9 mg/dL at 6-12 months (N=31), and by 18 mg/dL at > 12 months (N=20) of treatment.

Bipolar Mania

In a 4-week fixed dose study of adults with bipolar mania, mean changes from baseline in serum glucose and the proportion of patients with shifts in fasting glucose from Normal (<100 mg/dL) to High (≥126 mg/dL) for patients receiving FANAPT were similar to those for patients receiving placebo.

Dyslipidemia

Undesirable alterations in lipids have been observed in patients treated with atypical antipsychotics. Before or soon after initiation of antipsychotic medications, obtain a fasting lipid profile at baseline and monitor periodically during treatment.

Schizophrenia

In a 4-week fixed dose study of adults with schizophrenia, the mean change from baseline in fasted total cholesterol was 8.2 mg/dL and -2.2 mg/dL for FANAPT and placebo treated patients, respectively. The effects on LDL were similar to those on total cholesterol (changes of 9 mg/dL and -1.4 mg/dL for FANAPT and placebo treated patients, respectively). Mean changes from baseline in fasted triglycerides were -0.8 mg/dL and 16.5 mg/dL for FANAPT and placebo treated patients, respectively.

The proportion of patients with shifts from normal to high fasted total cholesterol, LDL, and triglycerides were similar for FANAPT and placebo-treated patients. The proportion of patients with shifts in fasted HDL from normal (≥40 mg/dL) to low (<40 mg/dL) was greater for placebo patients (23.8%) compared to patients treated with FANAPT (12.1%).

In pooled analysis from clinical studies, for adults with schizophrenia remaining on treatment with FANAPT, on average, both cholesterol and triglycerides decreased from baseline for adults with schizophrenia remaining on treatment at 3-6 months, 6-12 months, and >12-month time points in both 10-16 mg/day and 20-24 mg/day dose groups.

Bipolar Mania

In a 4-week fixed dose study of adults with bipolar mania, the mean changes from baseline for fasted total cholesterol, LDL, HDL, and triglycerides for FANAPT were similar to those for placebo-treated patients. The proportion of patients with shifts in fasted total cholesterol from normal (<200 mg/dL) to high (≥240 mg/dL) was greater for FANAPT treated patients (10.7%) than placebo-treated patients (7.2%). Shifts from normal to high LDL and triglycerides and from normal to low HDL occurred at rates for FANAPT similar to those for placebo treated patients.

Weight Gain

Weight gain has been observed with atypical antipsychotic use. Monitor weight at baseline and frequently thereafter.

Schizophrenia

Across all short- and long-term studies of adults with schizophrenia, the overall mean change from baseline at endpoint was 2.1 kg.

In 4 placebo-controlled, 4- or 6-week, fixed- or flexible-dose studies in adults with schizophrenia the mean change in weight (kg) was -0.1, 2, and 2.7 for placebo, FANAPT 10-16 mg/day, and FANAPT 20-24 mg/day groups, respectively. The proportion of patients with weight gain >7% increase from baseline was 4%, 12%, and 18% for placebo, FANAPT 10-16 mg/day, and FANAPT 20-24 mg/day groups, respectively.

Bipolar Mania

In a 4-week fixed dose study of adults with bipolar mania the mean change in weight (kg) was 1.6 and 4.6 kg for placebo and FANAPT 24 mg/day groups, respectively. The proportion of patients with weight gain ≥7% increase from baseline was 14% and 35%, for placebo and FANAPT 24 mg/day groups, respectively.

5.7 Orthostatic Hypotension and Syncope

FANAPT can induce orthostatic hypotension associated with dizziness, tachycardia, and syncope. This reflects its alpha1-adrenergic antagonist properties. In double-blind placebo-controlled short-term studies in patients with schizophrenia, where the dose was increased slowly, as recommended above, syncope was reported in 0.4% (5/1,344) of patients treated with FANAPT, compared with 0.2% (1/587) on placebo. Orthostatic hypotension was reported in 5% of patients given 20 mg to 24 mg/day, 3% of patients given 10 mg to 16 mg/day, and 1% of patients given placebo.

In a double-blind placebo-controlled short-term study in patients with bipolar mania, syncope was reported in 0.5% (1/206) of patients treated with FANAPT, compared with 0% (0/208) on placebo. In this study, orthostatic hypotension was reported in 4% (9/206) of patients treated with FANAPT and 2% (5/208) of patients given placebo.

More rapid titration would be expected to increase the rate of orthostatic hypotension and syncope.

Orthostatic vital signs should be monitored in patients who are vulnerable to hypotension (e.g., elderly patients, patients with dehydration, hypovolemia, and concomitant treatment with antihypertensive medications), patients with known cardiovascular disease (history of myocardial infarction, ischemic heart disease, heart failure, or conduction abnormalities), and patients with cerebrovascular disease.

5.8 Falls

Antipsychotics, including FANAPT, may cause somnolence, postural hypotension, motor and sensory instability, which may lead to falls and, consequently, fractures or other injuries. For patients with diseases, conditions, or medications that could exacerbate these effects, complete fall risk assessments when initiating antipsychotic treatment and recurrently for patients on long-term antipsychotic therapy.

5.9 Seizures

Like other antipsychotic drugs, FANAPT may cause seizures. The risk is greatest in patients with a history of seizures or with conditions that lower the seizure threshold. Conditions that lower the seizure threshold may be more prevalent in older patients.

5.10 Leukopenia, Neutropenia and Agranulocytosis

In clinical trial and postmarketing experience, leukopenia and neutropenia have been reported temporally related to antipsychotic agents. Agranulocytosis (including fatal cases) has also been reported.

Possible risk factors for leukopenia/neutropenia include preexisting low white blood cell count (WBC) and history of drug induced leukopenia/neutropenia. Patients with a pre-existing low WBC or a history of drug induced leukopenia/neutropenia should have their complete blood count (CBC) monitored frequently during the first few months of therapy and should discontinue FANAPT at the first sign of a decline in WBC in the absence of other causative factors.

Monitor patients with clinically significant neutropenia for fever or other symptoms or signs of infection and treat promptly if such symptoms or signs occur. Discontinue FANAPT in patients with absolute neutrophil count <1000/mm^3 and follow their WBC until recovery.

5.11 Hyperprolactinemia

As with other drugs that antagonize dopamine D2 receptors, FANAPT elevates prolactin levels.

Hyperprolactinemia may suppress hypothalamic GnRH, resulting in reduced pituitary gonadotropin secretion. This, in turn, may inhibit reproductive function by impairing gonadal steroidogenesis in both female and male patients. Galactorrhea, amenorrhea, gynecomastia, and impotence have been reported with prolactin-elevating compounds. Long-standing hyperprolactinemia when associated with hypogonadism may lead to decreased bone density in both female and male patients.

Tissue culture experiments indicate that approximately one-third of human breast cancers are prolactin-dependent in vitro, a factor of potential importance if the prescription of these drugs is contemplated in a patient with previously detected breast cancer. Mammary gland proliferative changes and increases in serum prolactin were seen in mice and rats treated with FANAPT [see Nonclinical Toxicology (13)]. Published epidemiologic studies have shown inconsistent results when exploring the potential association between hyperprolactinemia and breast cancer.

In a short-term placebo-controlled trial (4-weeks) in patients with schizophrenia, the mean change from baseline to endpoint in plasma prolactin levels for the FANAPT 24 mg/day-treated group was an increase of 2.6 ng/mL compared to a decrease of 6.3 ng/mL in the placebo-group. In placebo-controlled trials in patients with schizophrenia, elevated plasma prolactin levels (≥1.15xULN) were observed in 26% of adults treated with FANAPT compared to 12% in the placebo group. In the short-term trials, FANAPT was associated with modest levels of prolactin elevation compared to greater prolactin elevations observed with some other antipsychotic agents. In pooled analysis from clinical studies including longer term trials, in 3210 adults treated with iloperidone, gynecomastia was reported in 2 male subjects (0.1%) compared to 0% in placebo-treated patients, and galactorrhea was reported in 8 female subjects (0.2%) compared to 3 female subjects (0.5%) in placebo-treated patients.

In a short-term, placebo-controlled trial (4-weeks) in patients with bipolar mania, the mean change from baseline to endpoint in plasma prolactin levels for the FANAPT group was an increase of 15.66 ng/mL compared to a decrease of 0.58 ng/mL for the placebo group. In this trial, elevated plasma prolactin levels (≥1.15xULN) were observed in 35% of adults treated with FANAPT compared to 1% of the placebo group.

5.12 Body Temperature Regulation

Atypical antipsychotics may disrupt the body’s ability to reduce core body temperature. Strenuous exercise, exposure to extreme heat, dehydration, and anticholinergic medications may contribute to an elevation in core body temperature; use FANAPT with caution in patients who may experience these conditions.

5.13 Dysphagia

Esophageal dysmotility and aspiration have been associated with antipsychotic drug use. Aspiration pneumonia is a common cause of morbidity and mortality in elderly patients. Antipsychotic drugs, including FANAPT, should be used cautiously in patients at risk for aspiration.

5.14 Priapism

Four cases of priapism were reported in the pre-marketing FANAPT program (3 in the clinical studies for schizophrenia and 1 in the clinical study for manic and mixed episodes associated with bipolar I disorder). Drugs with alpha-adrenergic blocking effects have been reported to induce priapism. FANAPT shares this pharmacologic activity. Severe priapism may require surgical intervention.

5.15 Potential for Cognitive and Motor Impairment

FANAPT, like other antipsychotics, may cause somnolence and has the potential to impair judgment, thinking or motor skills. In short-term, placebo-controlled trials of schizophrenia, somnolence (including sedation) was reported in 12% (104/874) of adult patients treated with FANAPT at doses of 10 mg/day or greater versus 5.3% (31/587) treated with placebo. In a short-term, placebo-controlled trial of bipolar mania, somnolence (including sedation) was reported in 8% (16/206) of adult patients treated with FANAPT versus 3% (6/208) treated with placebo.

Patients should be cautioned about operating hazardous machinery, including motor vehicles, until they are reasonably certain that therapy with FANAPT does not affect them adversely.

5.16 Intraoperative Floppy Iris Syndrome (IFIS)

IFIS has been observed during cataract surgery in some patients on or previously treated with alpha-1 adrenergic blockers. This variant of small pupil syndrome is characterized by the combination of a flaccid iris that billows in response to intraoperative irrigation currents, progressive intraoperative miosis despite preoperative dilation with standard mydriatic drugs, and potential prolapse of the iris toward the phacoemulsification incisions. The patient’s surgeon should be prepared for possible modifications to their surgical technique, such as the utilization of iris hooks, iris dilator rings, or viscoelastic substances. There does not appear to be a benefit of stopping alpha1 blocker therapy prior to cataract surgery. The initiation of therapy with FANAPT in patients for whom cataract or glaucoma surgery is scheduled is not recommended.

6 ADVERSE REACTIONS

The following adverse reactions are discussed in more detail in other sections of the labeling:

- Increased Mortality in Elderly Patients with Dementia-Related Psychosis [see Warnings and Precautions (5.1)]
- Cerebrovascular Adverse Reactions, Including Stroke, in Elderly Patients with Dementia-Related Psychosis [see Warnings and Precautions (5.2)]
- QT Prolongation [see Warnings and Precautions (5.3)]
- Neuroleptic Malignant Syndrome (NMS) [see Warnings and Precautions (5.4)]
- Tardive Dyskinesia [see Warnings and Precautions (5.5)]
- Metabolic Changes [see Warnings and Precautions (5.6)]
- Orthostatic Hypotension and Syncope [see Warnings and Precautions (5.7)]
- Falls [see Warnings and Precautions (5.8)]
- Seizures [see Warnings and Precautions (5.9)]
- Leukopenia, Neutropenia and Agranulocytosis [see Warnings and Precautions (5.10)]
- Hyperprolactinemia [see Warnings and Precautions (5.11)]
- Body Temperature Regulation [see Warnings and Precautions (5.12)]
- Dysphagia [see Warnings and Precautions (5.13)]
- Priapism [see Warnings and Precautions (5.14)]
- Potential for Cognitive and Motor Impairment [see Warnings and Precautions (5.15)]
- Intraoperative Floppy Iris Syndrome [see Warnings and Precautions (5.16)]

6.1 Clinical Studies Experience

Because clinical trials are conducted under widely varying conditions, adverse reaction rates observed in the clinical trial of a drug cannot be directly compared to rates in the clinical trials of another drug and may not reflect the rates observed in clinical practice.

The information below is derived from a clinical trial database for FANAPT consisting of 3,229 patients exposed to FANAPT at doses of 10 mg/day or greater, for the treatment of schizophrenia and from a clinical trial database for FANAPT consisting of 312 patients exposed to FANAPT at doses of 24 mg/day, for the treatment of bipolar mania [see Clinical Studies (14.2)]. Of these, 999 received FANAPT for at least 6 months, with 657 exposed to FANAPT for at least 12 months for the treatment of schizophrenia and 69 received FANAPT for at least 6 months, with 28 exposed to FANAPT for at least 12 months for the treatment of bipolar mania. All of these patients who received FANAPT were participating in multiple-dose clinical trials. The conditions and duration of treatment with FANAPT varied greatly and included (in overlapping categories), open-label and double-blind phases of studies, inpatients and outpatients, fixed-dose and flexible-dose studies, and short-term and longer-term exposure.

Schizophrenia

The information presented in this section was derived from pooled data from 4 placebo-controlled, 4- or 6-week, fixed- or flexible-dose studies in patients who received FANAPT at daily doses within a range of 10 to 24 mg (n=874).

Adverse Reactions Occurring at an Incidence of 2% or More among FANAPT-Treated Patients and More Frequent than Placebo

Table 3 enumerates the pooled incidences of adverse reactions that were spontaneously reported in four placebo-controlled, 4- or 6-week, fixed- or flexible-dose studies, listing those reactions that occurred in 2% or more of patients treated with FANAPT in any of the dose groups, and for which the incidence in FANAPT- treated patients in any dose group was greater than the incidence in patients treated with placebo.

Table 3: Percentage of Adverse Reactions in Short-Term, Fixed- or Flexible-Dose, Placebo- Controlled Schizophrenia Trials in Adult Patients*

Body System or Organ Class | Placebo (%) | FANAPT 10-16 mg/day (%) | FANAPT 20-24 mg/day (%)
Dictionary-derived Term | (N=587) | (N=483) | (N=391)
Body as a Whole
Arthralgia | 2 | 3 | 3
Fatigue | 3 | 4 | 6
Musculoskeletal Stiffness | 1 | 1 | 3
Weight Increased | 1 | 1 | 9
Cardiac Disorders
Tachycardia | 1 | 3 | 12
Eye Disorders
Vision Blurred | 2 | 3 | 1
Gastrointestinal Disorders
Nausea | 8 | 7 | 10
Dry Mouth | 1 | 8 | 10
Diarrhea | 4 | 5 | 7
Abdominal Discomfort | 1 | 1 | 3
Infections
Nasopharyngitis | 3 | 4 | 3
Upper Respiratory Tract Infection | 1 | 2 | 3
Nervous System Disorders
Dizziness | 7 | 10 | 20
Somnolence | 5 | 9 | 15
Extrapyramidal Disorder | 4 | 5 | 4
Tremor | 2 | 3 | 3
Lethargy | 1 | 3 | 1
Reproductive System
Ejaculation Failure | <1 | 2 | 2
Respiratory
Nasal Congestion | 2 | 5 | 8
Dyspnea | <1 | 2 | 2
Skin
Rash | 2 | 3 | 2
Vascular Disorders
Orthostatic Hypotension | 1 | 3 | 5
Hypotension | <1 | <1 | 3
* Table includes adverse reactions that were reported in 2% or more of patients in any of the FANAPT dose groups and which occurred at greater incidence than in the placebo group. Figures rounded to the nearest integer.

Bipolar Mania

Table 4 enumerates the adverse reactions that occurred at an incidence of ≥2% and greater than placebo in a placebo-controlled, 4-week bipolar mania trial with FANAPT.

Table 4: Adverse Reactions Occurring in ≥2% of Adult Patients Treated with FANAPT and > Placebo in a Short-Term, Fixed-Dose, Placebo-Controlled Bipolar Mania Trial

System Organ Class Preferred Terms | Placebo N=208 % | FANAPT 24 mg/day** N=206 %
Cardiac disorders
Tachycardia* | 5 | 23
Gastrointestinal disorders
Dry mouth | 2 | 9
Nausea* | 3 | 4
Investigations
Hepatic enzyme increased* | 1 | 8
Weight increased* | 1 | 6
Nervous system disorders
Dizziness* | 1 | 12
Headache* | 4 | 5
Somnolence* | 3 | 8
Akathisia | 0 | 4
Renal and urinary disorders
Urinary urgency and Polyuria* | 0 | 3
Reproductive system and breast disorders
Sexual Dysfunction* | 0.5 | 4
Respiratory, thoracic, and mediastinal disorders
Nasal congestion | 1 | 6
Vascular disorders
Hypotension* | 3 | 6
General disorders and administration site conditions
Fatigue* | 1 | 3
*The following terms were combined:
Tachycardia includes: heart rate increased, sinus tachycardia, postural orthostatic tachycardia syndrome, and tachycardia
Nausea includes: nausea and vomiting
Hepatic enzyme increased includes: predominantly alanine aminotransferase increased and including aspartate aminotransferase increased, hepatic enzyme increased, and transaminase increased)
Weight increased includes: weight increased and BMI increased.
Dizziness includes: dizziness and postural dizziness
Headache includes: Headache and Tension headache
Somnolence includes: predominantly sedation and including sedation complication and somnolence
Urinary urgency and Polyuria includes: hypertonic bladder, micturition urgency, polyuria, and urinary incontinence
Sexual Dysfunction includes: ejaculation failure, erectile dysfunction, retrograde ejaculation, and ejaculation delayed
Hypotension includes: orthostatic hypotension
Fatigue includes: lethargy
**Patients with poor CYP2D6 metabolizer status received 12 mg/day.

Dose-Related Adverse Reactions in Clinical Trials

Based on the pooled data from 4 placebo-controlled, 4- or 6-week, fixed- or flexible-dose studies, adverse reactions in patients with schizophrenia that occurred with a greater than 2% incidence in the patients treated with FANAPT, and for which the incidence in patients treated with FANAPT 20-24 mg/day were twice than the incidence in patients treated with FANAPT 10-16 mg/day were: abdominal discomfort, dizziness, hypotension, musculoskeletal stiffness, tachycardia, and weight increased.

Common and Drug-Related Adverse Reactions in Clinical Trials

Based on the pooled data from 4 placebo-controlled, 4- or 6-week, fixed- or flexible-dose studies of patients with schizophrenia, the following adverse reactions occurred in ≥5% incidence in the patients treated with FANAPT and at least twice the placebo rate for at least 1 dose: dizziness, dry mouth, fatigue, nasal congestion, somnolence, tachycardia, orthostatic hypotension, and weight increased. Dizziness, tachycardia, and weight increased were at least twice as common on 20-24 mg/day as on 10-16 mg/day.

In a short-term, placebo-controlled trial in patients with bipolar mania the following adverse reactions occurred in ≥5% incidence in the patients treated with FANAPT and at least twice the placebo rate: tachycardia, dizziness, dry mouth, hepatic enzymes increased, nasal congestion, weight increased, hypotension, and somnolence.

Extrapyramidal Symptoms (EPS) in Clinical Trials

Pooled data from the 4 placebo-controlled, 4- or 6-week, fixed- or flexible-dose studies of patients with schizophrenia provided information regarding EPS. Adverse event data collected from those trials showed the following rates of EPS-related adverse events as shown in Table 5.

Table 5: Percentage of EPS Compared to Placebo in 4- or 6-week Schizophrenia Trials

 | Placebo (%) | FANAPT 10-16 mg/day (%) | FANAPT 20-24 mg/day (%)
Preferred Term | (N=587) | (N=483) | (N=391)
All EPS events | 11.6 | 13.5 | 15.1
Tremor | 1.9 | 2.5 | 3.1
Akathisia | 2.7 | 1.7 | 2.3
Dyskinesia | 1.5 | 1.7 | 1
Dystonia | 0.7 | 1 | 0.8
Bradykinesia | 0 | 0.6 | 0.5
Parkinsonism | 0 | 0.2 | 0.3

Table 6 shows the rates of EPS-related events in a 4-week bipolar mania trial.

Table 6: Percentage of EPS Compared to Placebo in a 4-week Bipolar Mania Trial

Preferred Term | Placebo (%) | FANAPT 24 mg/day* (%)
 | N=208 | N=206
All EPS events | 0 | 8.3
Akathisia | 0 | 4.4
Extrapyramidal Disorder | 0 | 1
Blepharospasm | 0 | 0.5
Dystonia | 0 | 0.5
Muscle Spasm | 0 | 0.5
Restlessness | 0 | 0.5
Torticollis | 0 | 0.5
Tremor | 0 | 0.5
*Patients with poor CYP2D6 metabolizer status received 12 mg/day.

Adverse Reactions Associated with Discontinuation of Treatment in Clinical Trials

Based on the pooled data from 4 placebo-controlled, 4- or 6-week, fixed- or flexible-dose studies in patients with schizophrenia, there was no difference in the incidence of discontinuation due to adverse reactions between FANAPT-treated (5%) and placebo-treated (5%) patients. The types of adverse reactions that led to discontinuation were similar for the FANAPT- and placebo-treated patients.

In a 4-week, placebo-controlled study in patients with bipolar mania, the incidence of discontinuation due to adverse reactions was higher in FANAPT-treated (8.7%) patients than placebo-treated (5.3%) patients. Adverse reactions that led to discontinuation in more than one FANAPT-treated subject were liver enzyme elevations, nausea and vomiting, dizziness and hypotension.

Demographic Differences in Adverse Reactions in Clinical Trials

An examination of population subgroups in the 4 placebo-controlled, 4- or 6-week, fixed- or flexible-dose studies of patients with schizophrenia did not reveal any evidence of differences in safety on the basis of age, sex or race.

Laboratory Test Abnormalities in Clinical Trials

There were no differences between FANAPT and placebo in the incidence of discontinuation due to changes in hematology, or urinalysis.

Serum Transaminases

In a short-term placebo-controlled trial, asymptomatic alanine aminotransferase (ALT) elevations ≥3x ULN occurred in 9.2% of FANAPT-treated patients with acute mania compared to 1.5% of placebo treated subjects. AST elevations were less common.

Hematocrit

In short-term placebo-controlled trials (4- to 6-weeks) in patients with schizophrenia, there were 1.0% (13/1342) FANAPT-treated patients with hematocrit at least one time below the extended normal range during post-randomization treatment, compared to 0.3% (2/585) on placebo. The extended normal range for lowered hematocrit was defined in each of these trials as the value 15% below the normal range for the centralized laboratory that was used in the trial.

In a short-term placebo-controlled trial (4 weeks) in patients with bipolar mania, there were 3.5% (7/200) FANAPT-treated patients with hematocrit at least one time below the extended normal range (<0.85xLLN) during post-randomization treatment, compared to 0.5% (1/196) on placebo.

Analysis of clinical laboratory data following administration of FANAPT suggested the mechanism of hemodilution based on consistent decreases in hematocrit, hemoglobin, white blood cells, total protein, and albumin. Decreases in hematocrit and total protein have been observed with other alpha receptor antagonists and are attributed to hemodilution [see Clinical Pharmacology (12.2)]

Serum Urate Levels

In a 4-week placebo-controlled trial in patients with bipolar mania, treatment with FANAPT 12 mg twice a day resulted in an increase of serum urate levels of approximately 27.2 umol/L (0.457 mg/dL) compared to 0.1 umol/L (0.002 mg/dL) in placebo group.

Other Reactions During the Pre-marketing Evaluation of FANAPT

Patients with Schizophrenia

The following is a list of MedDRA terms that reflect adverse reactions in patients treated with FANAPT at multiple doses ≥ 4 mg/day during any phase of a trial with the database of 3,210 FANAPT-treated patients with schizophrenia. All reported reactions are included except those already listed in Table 3, or other parts of the Adverse Reactions (6), those considered in the Warnings and Precautions (5), those reaction terms which were so general as to be uninformative, reactions reported in fewer than 3 patients and which were neither serious nor life-threatening, reactions that are otherwise common as background reactions, and reactions considered unlikely to be drug related.

Reactions are further categorized by MedDRA system organ class and listed in order of decreasing frequency according to the following definitions: frequent adverse events are those occurring in at least 1/100 patients (only those not listed in Table 3 appear in this listing); infrequent adverse reactions are those occurring in 1/100 to 1/1000 patients; rare events are those occurring in fewer than 1/1000 patients.

Blood and Lymphatic Disorders: Infrequent – anemia, iron deficiency anemia; Rare – leukopenia

Cardiac Disorders: Frequent – palpitations; Rare – arrhythmia, atrioventricular block first degree, cardiac failure (including congestive and acute)

Ear and Labyrinth Disorders: Infrequent – vertigo, tinnitus

Endocrine Disorders: Infrequent – hypothyroidism

Eye Disorders: Frequent – conjunctivitis (including allergic); Infrequent – dry eye, blepharitis, eyelid edema, eye swelling, lenticular opacities, cataract, hyperemia (including conjunctival)

Gastrointestinal Disorders: Infrequent – gastritis, salivary hypersecretion, fecal incontinence, mouth ulceration; Rare – aphthous stomatitis, duodenal ulcer, hiatus hernia, hyperchlorhydria, lip ulceration, reflux esophagitis, stomatitis

General Disorders and Administrative Site Conditions: Infrequent – edema (general, pitting, due to cardiac disease), difficulty in walking, thirst; Rare – hyperthermia

Hepatobiliary Disorders: Infrequent – cholelithiasis

Investigations: Frequent: weight decreased; Infrequent – hemoglobin decreased, neutrophil count increased, hematocrit decreased

Metabolism and Nutrition Disorders: Infrequent – increased appetite, dehydration, hypokalemia, fluid retention

Musculoskeletal and Connective Tissue Disorders: Frequent – myalgia, muscle spasms; Rare – torticollis

Nervous System Disorders: Infrequent – paresthesia, psychomotor hyperactivity, restlessness, amnesia, nystagmus; Rare – restless legs syndrome

Psychiatric Disorders: Frequent – restlessness, aggression, delusion; Infrequent – hostility, libido decreased, paranoia, anorgasmia, confusional state, mania, catatonia, mood swings, panic attack, obsessive-compulsive disorder, bulimia nervosa, delirium, polydipsia psychogenic, impulse-control disorder, major depression

Renal and Urinary Disorders: Frequent – urinary incontinence; Infrequent – dysuria, pollakiuria, enuresis, nephrolithiasis; Rare – urinary retention, renal failure acute

Reproductive System and Breast Disorders: Frequent – erectile dysfunction; Infrequent – testicular pain, amenorrhea, breast pain; Rare – menstruation irregular, gynecomastia, menorrhagia, metrorrhagia, postmenopausal hemorrhage, prostatitis

Respiratory, Thoracic and Mediastinal Disorders: Infrequent – epistaxis, asthma, rhinorrhea, sinus congestion, nasal dryness; Rare – dry throat, sleep apnea syndrome, dyspnea exertional

6.2 Postmarketing Experience

The following adverse reactions have been identified during post-approval use of FANAPT. Because these reactions are reported voluntarily from a population of uncertain size, it is not always possible to estimate their frequency or establish a causal relationship to drug exposure: retrograde ejaculation and hypersensitivity reactions (including anaphylaxis; angioedema; throat tightness; oropharyngeal swelling; swelling of the face, lips, mouth, and tongue; urticaria; rash; and pruritus).

7 DRUG INTERACTIONS

7.1 Clinically Important Drug Interactions with FANAPT

Table 7 presents clinically important drug interactions with FANAPT.

Table 7: Clinically Important Drug Interactions with FANAPT

Strong CYP2D6 Inhibitors
Clinical Impact | Coadministration of fluoxetine with iloperidone increased exposure (area under curve, [AUC]) of iloperidone and its metabolite P88, by about 2- to 3- fold, and decreased the AUC of its metabolite P95 by one-half [see Clinical Pharmacology (12.3, 12.5)].; Coadministration of paroxetine with iloperidone resulted in increased mean steady-state peak concentrations of iloperidone and its metabolite P88, by about 1.6- fold, and decreased mean steady-state peak concentrations of its metabolite P95 by one-half [see Clinical Pharmacology (12.3, 12.5)].
Intervention | Reduce the dose of FANAPT by one-half when administered with strong CYP2D6 inhibitors. When a strong CYP2D6 inhibitor is withdrawn from the combination therapy, the iloperidone dose should be returned to the previous level [see Dosage and Administration (2.4)].
Strong CYP3A4 Inhibitors
Clinical Impact | Co-administration of ketoconazole with iloperidone, increased the AUC of iloperidone and its metabolites P88 and P95 by 57%, 55%, and 35%, respectively [see Clinical Pharmacology (12.3)].
Intervention | Reduce the dose of FANAPT by one-half when administered with strong CYP3A4 inhibitors. When the CYP3A4 inhibitor is withdrawn from the combination therapy, the FANAPT dose should be returned to the previous level [see Dosage and Administration (2.4)].
Concomitant use of Strong CYP2D6 and Strong CYP3A4 Inhibitors
Clinical Impact | Coadministration of iloperidone with paroxetine and ketoconazole resulted in a 1.4- fold increase in steady-state concentrations of iloperidone and its metabolite P88 and a 1.4- fold decrease in the P95 in the presence of paroxetine [see Clinical Pharmacology (12.3)].
Intervention | Coadministration of FANAPT with inhibitors of both CYP2D6 and CYP3A4 did not add to the effect of either inhibitor given alone. Reduce the dose of FANAPT by about one-half if administered concomitantly with both a CYP2D6 and CYP3A4 inhibitor same as if it is coadministered with only one inhibitor. When the inhibitors of CYP2D6 and CYP3A4 are withdrawn from the combination therapy, the FANAPT dose should be returned to the previous level [see Dosage and Administration (2.4)].

7.2 Drugs that Prolong the QT Interval

Concomitant use of drugs that prolong the QT interval may add to the QT effects of FANAPT and increase the risk of cardiac arrhythmia. Avoid the use of FANAPT in combination with any other drugs that prolong the QT interval [see Warnings and Precautions (5.3)].

7.3 Drugs that Lower Blood Pressure

Concomitant use of FANAPT with medications that lower blood pressure could potentially cause symptomatic hypotension. Avoid coadministration of FANAPT with alpha-adrenergic blocking agents and adjust medications that affect blood pressure as needed [see Warnings and Precautions (5.7)].

8 USE IN SPECIFIC POPULATIONS

8.1 Pregnancy

Pregnancy Exposure Registry

There is a pregnancy exposure registry that monitors pregnancy outcomes in women exposed to FANAPT during pregnancy. For more information contact the National Pregnancy Registry for Atypical Antipsychotics at 1-866-961-2388 or visit http://womensmentalhealth.org/clinical-and-research-programs/pregnancyregistry/.

Risk Summary

Neonates whose mothers are exposed to antipsychotic drugs, including FANAPT, during the third trimester of pregnancy are at risk for extrapyramidal and/or withdrawal symptoms following delivery [see Clinical Considerations]. The limited available data with FANAPT in pregnant women are not sufficient to inform a drug-associated risk for major birth defects and miscarriage. Iloperidone was not teratogenic when administered orally to pregnant rats during organogenesis at doses up to 26 times the maximum recommended human dose of 24 mg/day on mg/m^2 basis. However, it prolonged the duration of pregnancy and parturition, increased still births, early intrauterine deaths, increased incidence of developmental delays, and decreased post-partum pup survival. Iloperidone was not teratogenic when administered orally to pregnant rabbits during organogenesis at doses up to 20-times the MRHD on mg/m^2 basis. However, it increased early intrauterine deaths and decreased fetal viability at term at the highest dose which was also a maternally toxic dose [see Data].

The background risk of major birth defects and miscarriage for the indicated population is unknown. In the U.S. general population, the estimated background risk of major birth defects and miscarriage in clinically recognized pregnancies is 2 to 4% and 15 to 20%, respectively.

Clinical Considerations

Fetal/Neonatal Adverse Reactions

Extrapyramidal and/or withdrawal symptoms, including agitation, hypertonia, hypotonia, tremor, somnolence, respiratory distress and feeding disorder have been reported in neonates whose mothers were exposed to antipsychotic drugs during the third trimester of pregnancy. These symptoms have varied in severity. Some neonates recovered within hours or days without specific treatment; others required prolonged hospitalization. Monitor neonates for extrapyramidal and/or withdrawal symptoms and manage symptoms appropriately.

Data

Animal Data

In an embryo-fetal development study, pregnant rats were given 4, 16, or 64 mg/kg/day (1.6, 6.5, and 26 times the maximum recommended human dose (MRHD) of 24 mg/day on a mg/m^2 basis) of iloperidone orally during the period of organogenesis. The highest dose caused increased early intrauterine deaths, decreased fetal weight and length, decreased fetal skeletal ossification, and an increased incidence of minor fetal skeletal anomalies and variations; this dose also caused decreased maternal food consumption and weight gain.

In an embryo-fetal development study, pregnant rabbits were given 4, 10, or 25 mg/kg/day (3, 8, and 20 times the MRHD on a mg/m^2 basis) of iloperidone during the period of organogenesis. The highest dose caused increased early intrauterine deaths and decreased fetal viability at term; this dose also caused maternal toxicity.

In additional studies in which rats were given iloperidone at doses similar to the above beginning from either pre-conception or from day 17 of gestation and continuing through weaning, adverse reproductive effects included prolonged pregnancy and parturition, increased stillbirth rates, increased incidence of fetal visceral variations, decreased fetal and pup weights, and decreased post-partum pup survival. There were no drug effects on the neurobehavioral or reproductive development of the surviving pups. No-effect doses ranged from 4 to 12 mg/kg except for the increase in stillbirth rates which occurred at the lowest dose tested of 4 mg/kg, which is 1.6 times the MRHD on a mg/m^2 basis. Maternal toxicity was seen at the higher doses in these studies.

The iloperidone metabolite P95, which is a major circulating metabolite of iloperidone in humans but is not present in significant amounts in rats, was given to pregnant rats during the period of organogenesis at oral doses of 20, 80, or 200 mg/kg/day. No teratogenic effects were seen. Delayed skeletal ossification occurred at all doses. No significant maternal toxicity was produced. Plasma levels of P95 (AUC) at the highest dose tested were 2 times those in humans receiving the MRHD of iloperidone.

8.2 Lactation

Risk Summary

There is no information regarding the presence of iloperidone or its metabolites in human milk, the effects of iloperidone on a breastfed child, nor the effects of iloperidone on human milk production. Iloperidone is present in rat milk [see Data]. Because of the potential for serious adverse reactions in breastfed infants, advise a woman not to breastfeed during treatment with FANAPT.

Data

The transfer of radioactivity into the milk of lactating rats was investigated following a single dose of [14C] iloperidone at 5 mg/kg. The concentration of radioactivity in milk at 4 hours post-dose was near 10-fold greater than that in plasma at the same time. However, by 24 hours after dosing, concentrations of radioactivity in milk had fallen to values slightly lower than plasma. The metabolic profile in milk was qualitatively similar to that in plasma.

8.4 Pediatric Use

Safety and effectiveness of FANAPT have not been established in pediatric patients.

8.5 Geriatric Use

Clinical Studies of FANAPT in the treatment of schizophrenia did not include sufficient numbers of patients aged 65 years and over to determine whether or not they respond differently than younger adult patients. Of the 3,210 patients with schizophrenia treated with FANAPT in clinical trials, 25 (0.5%) were ≥65 years old and there were no patients ≥75 years old. Of the 206 patients with bipolar mania treated with FANAPT in a clinical trial, 2 (0.1%) were 65 years old and there were no patients were >65 years old.

Elderly patients with dementia-related psychosis treated with FANAPT are at an increased risk of death compared to placebo. FANAPT is not approved for the treatment of patients with dementia-related psychosis [see Boxed Warning and Warnings and Precautions (5.1, 5.2)].

8.6 Hepatic Impairment

No dose adjustment to FANAPT is needed in patients with mild hepatic impairment (Child-Pugh class A). Patients with moderate hepatic impairment (Child-Pugh class B) may require dose reduction. FANAPT is not recommended for patients with severe hepatic impairment (Child-Pugh class C) [see Dosage and Administration (2.3), Clinical Pharmacology (12.3)].

9 DRUG ABUSE AND DEPENDENCE

9.1 Controlled Substance

FANAPT is not a controlled substance.

9.2 Abuse

FANAPT has not been systematically studied in animals or humans for its potential for abuse, tolerance, or physical dependence. While the clinical trials did not reveal any tendency for drug-seeking behavior, these observations were not systematic and it is not possible to predict on the basis of this experience the extent to which a CNS active drug, FANAPT, will be misused, diverted, and/or abused once marketed. Consequently, patients should be evaluated carefully for a history of drug abuse, and such patients should be observed closely for signs of FANAPT misuse or abuse (e.g. development of tolerance, increases in dose, drug-seeking behavior).

10 OVERDOSAGE

10.1 Human Experience

In pre-marketing trials involving over 3,522 patients, accidental or intentional overdose of FANAPT was documented in 8 patients ranging from 48 mg to 576 mg taken at once and 292 mg taken over a 3-day period. No fatalities were reported from these cases. The largest confirmed single ingestion of FANAPT was 576 mg; no adverse physical effects were noted for this patient. The next largest confirmed ingestion of FANAPT was 438 mg over a 4-day period; extrapyramidal symptoms and a QTc interval of 507 msec were reported for this patient with no cardiac sequelae. This patient resumed FANAPT treatment for an additional 11 months. In general, reported signs and symptoms were those resulting from an exaggeration of the known pharmacological effects (e.g., drowsiness and sedation, tachycardia and hypotension) of FANAPT.

10.2 Management of Overdose

There is no specific antidote for FANAPT. Therefore appropriate supportive measures should be instituted. In case of acute overdose, the healthcare provider should establish and maintain an airway and ensure adequate oxygenation and ventilation. Gastric lavage (after intubation, if patient is unconscious) and administration of activated charcoal together with a laxative should be considered. The possibility of obtundation, seizures or dystonic reaction of the head and neck following overdose may create a risk of aspiration with induced emesis. Cardiovascular monitoring should commence immediately and should include continuous ECG monitoring to detect possible arrhythmias. If antiarrhythmic therapy is administered, disopyramide, procainamide and quinidine should not be used, as they have the potential for QT-prolonging effects that might be additive to those of FANAPT. Similarly, it is reasonable to expect that the alpha-blocking properties of bretylium might be additive to those of FANAPT, resulting in problematic hypotension. Hypotension and circulatory collapse should be treated with appropriate measures such as intravenous fluids or sympathomimetic agents (epinephrine and dopamine should not be used, since beta stimulation may worsen hypotension in the setting of FANAPT-induced alpha blockade). In cases of severe extrapyramidal symptoms, anticholinergic medication should be administered. Close medical supervision should continue until the patient recovers.

Consider contacting the Poison Help Line (1-800-222-1222) or a medical toxicologist for additional overdose management recommendations.

11 DESCRIPTION

FANAPT is an atypical antipsychotic belonging to the chemical class of piperidinyl-benzisoxazole derivatives. Its chemical name is 4’-[3-[4-(6-Fluoro-1,2-benzisoxazol-3-yl)piperidino]propoxy]-3’-methoxyacetophenone. Its molecular formula is C24H27FN2O4 and its molecular weight is 426.48. The structural formula is:

Iloperidone is a white to off-white finely crystalline powder. It is practically insoluble in water, very slightly soluble in 0.1 N HCl and freely soluble in chloroform, ethanol, methanol, and acetonitrile.

FANAPT tablets are intended for oral administration only. Each round, uncoated tablet contains 1 mg, 2 mg, 4 mg, 6 mg, 8 mg, 10 mg, or 12 mg of iloperidone. Inactive ingredients are: lactose monohydrate, microcrystalline cellulose, hydroxypropylmethylcellulose, crospovidone, magnesium stearate, colloidal silicon dioxide, and purified water (removed during processing). The tablets are white, round, flat, beveled-edged, and identified with a logo “” debossed on one side and tablet strength “1”, “2”, “4”, “6”, “8”, “10”, or “12” debossed on the other side.

12 CLINICAL PHARMACOLOGY

12.1 Mechanism of Action

The mechanism of action of iloperidone in schizophrenia and bipolar I disorder is unknown. However, the efficacy of iloperidone could be mediated through a combination of dopamine type 2 (D2) and serotonin type 2 (5-HT2) antagonism. Iloperidone forms an active metabolite, P88, that has an in vitro receptor binding profile similar to the parent drug.

12.2 Pharmacodynamics

Iloperidone acts as an antagonist with high (nM) affinity binding to serotonin 5-HT2A,dopamine D2 and D3 receptors, and norepinephrine NEα1 receptors (Ki values of 5.6, 6.3, 7.1, and 0.36 nM, respectively). Iloperidone has moderate affinity for dopamine D4, and serotonin 5-HT6 and 5-HT7 receptors (Ki values of 25, 43, and 22, nM respectively), and low affinity for the serotonin 5-HT1A, dopamine D1, and histamine H1 receptors (Ki values of 168, 216, and 437 nM, respectively). Iloperidone has no appreciable affinity (Ki >1000 nM) for cholinergic muscarinic receptors. The affinity of iloperidone metabolite P88 is generally equal to or less than that of the parent compound, while the metabolite P95 only shows affinity for 5-HT2A (Ki value of 3.91) and the NEα1A, NEα1B, NEα1D, and NEα2C receptors (Ki values of 4.7, 2.7, 8.8, and 4.7 nM respectively).

12.3 Pharmacokinetics

The pharmacokinetics of iloperidone is more than dose proportional. Steady-state concentrations are attained within 3 to 4 days of dosing. Iloperidone accumulation is predictable from single-dose pharmacokinetics.

Absorption

Iloperidone is well absorbed after administration of the tablet with time to peak plasma concentrations (Tmax) occurring within 2 to 4 hours. The relative bioavailability of the tablet formulation compared to oral solution is 96%.

Effect of Food

Administration of iloperidone with a standard high-fat meal did not significantly affect the Cmax or AUC of iloperidone, P88, or P95, but delayed Tmax by 1 hour for iloperidone, 2 hours for P88 and 6 hours for P95. FANAPT can be administered without regard to meals.

Distribution

Iloperidone has an apparent volume of distribution of 1340-2800 L. At therapeutic concentrations, the unbound fraction of iloperidone in plasma is ~3% and of each metabolite (P88 and P95) it is ~8%.

Elimination

The observed mean elimination half-lives for iloperidone, P88, and P95 in CYP2D6 extensive metabolizers (EM) are 18, 26, and 23 hours, respectively, and in poor metabolizers (PM) are 33, 37, and 31 hours, respectively.

Iloperidone has an apparent clearance (clearance / bioavailability) of 47 to 102 L/h.

Metabolism

Elimination of iloperidone is mainly through hepatic metabolism. Iloperidone is metabolized primarily by 3 biotransformation pathways: carbonyl reduction, hydroxylation (mediated by CYP2D6) and O-demethylation (mediated by CYP3A4). There are 2 predominant iloperidone metabolites, P95 and P88. The iloperidone metabolite P95 represents 47.9% of the AUC of iloperidone and its metabolites in plasma at steady-state for extensive metabolizers (EM) and 25% for poor metabolizers (PM). The active metabolite P88 accounts for 19.5% and 34.0% of total plasma exposure in EM and PM, respectively.

Approximately 7% - 10% of Caucasians and 3% - 8% of black/African Americans lack the capacity to metabolize CYP2D6 substrates and are classified as poor metabolizers (PM), whereas the rest are intermediate, extensive, or ultrarapid metabolizers.

Excretion

The bulk of the radioactive materials were recovered in the urine (mean 58.2% and 45.1% in EM and PM, respectively), with feces accounting for 19.9% (EM) to 22.1% (PM) of the dosed radioactivity.

Specific Populations

Patients with Renal Impairment

Renal impairment (creatinine clearance <30 mL/min) had minimal effect on Cmax of iloperidone (given in a single dose of 3 mg) and its metabolites P88 and P95 in any of the 3 analytes measured. AUC0–∞ was increased by 24%, decreased by 6%, and increased by 52% for iloperidone, P88 and P95, respectively, in subjects with renal impairment.

Patients with Hepatic Impairment

In adult subjects with mild hepatic impairment, no relevant difference in pharmacokinetics of iloperidone, P88 or P95 (total or unbound) was observed compared to healthy adult controls. In subjects with moderate hepatic impairment a higher (2-fold) and more variable free exposure to the active metabolites P88 was observed compared to healthy controls, whereas exposure to iloperidone and P95 was generally similar (less than 50% change compared to control). Studies with severe liver impaired subjects have not been conducted [see Dosage and Administration (2.3), Use in Specific Populations (8.6)].

Effect of Smoking

Based on in vitro studies utilizing human liver enzymes, FANAPT is not a substrate for CYP1A2; smoking should therefore not have an effect on the pharmacokinetics of FANAPT.

Drug Interactions Studies

CYP2D6 and CYP3A4 Inhibitors

The effects of fluoxetine and ketoconazole on the exposures of FANAPT, P88, and P95 are summarized in Figure 1.

Figure 1: Effect of CYP3A4 and CYP2D6 Inhibitors on the Pharmacokinetics of FANAPT and its Metabolites

Ketoconazole: Co-administration of ketoconazole (200 mg twice daily for 4 days), a potent inhibitor of CYP3A4, with a 3 mg single dose of iloperidone to 19 healthy volunteers, ages 18-45 years, increased the area under the curve (AUC) of iloperidone and its metabolites P88 and P95 by 57%, 55% and 35%, respectively. Weaker inhibitors (e.g., erythromycin, grapefruit juice) have not been studied.

Fluoxetine: Coadministration of fluoxetine (20 mg twice daily for 21 days), a potent inhibitor of CYP2D6, with a single 3 mg dose of iloperidone to 23 healthy volunteers, ages 29-44 years, who were classified as CYP2D6 extensive metabolizers, increased the AUC of iloperidone and its metabolite P88, by about 2- to 3- fold, and decreased the AUC of its metabolite P95 by one-half.

Paroxetine: Coadministration of paroxetine (20 mg/day for 5-8 days), a potent inhibitor of CYP2D6, with multiple doses of iloperidone (8 or 12 mg twice daily) to patients with schizophrenia ages 18-65 years resulted in increased mean steady-state peak concentrations of iloperidone and its metabolite P88, by about 1.6 fold, and decreased mean steady-state peak concentrations of its metabolite P95 by one-half.

Paroxetine and Ketoconazole: Coadministration of paroxetine (20 mg once daily for 10 days), a CYP2D6 inhibitor, and ketoconazole (200 mg twice daily) with multiple doses of iloperidone (8 or 12 mg twice daily) to patients with schizophrenia ages 18-65 years resulted in a 1.4 fold increase in steady-state concentrations of iloperidone and its metabolite P88 and a 1.4 fold decrease in the P95 in the presence of paroxetine.

Dextromethorphan: A study in healthy volunteers showed that changes in the pharmacokinetics of dextromethorphan (80 mg dose) when a 3 mg dose of iloperidone was co-administered resulted in a 17% increase in total exposure and a 26% increase in the maximum plasma concentrations Cmax of dextromethorphan. Thus, an interaction between iloperidone and other CYP2D6 substrates is unlikely.

Fluoxetine: A single 3 mg dose of iloperidone had no effect on the pharmacokinetics of fluoxetine (20 mg twice daily).

Midazolam (a sensitive CYP 3A4 substrate): A study in patients with schizophrenia showed a less than 50% increase in midazolam total exposure at iloperidone steady state (14 days of oral dosing at up to 10 mg iloperidone twice daily) and no effect on midazolam Cmax. Thus, an interaction between iloperidone and other CYP3A4 substrates is unlikely.

In Vitro Studies

Based on the in vitro data, iloperidone is not a substrate for CYP1A1, CYP1A2, CYP2A6, CYP2B6, CYP2C8, CYP2C9, CYP2C19, or CYP2E1 enzymes. This suggests that an interaction of iloperidone with inhibitors or inducers of these enzymes, or other factors, like smoking, is unlikely.

In vitro studies in human liver microsomes showed that iloperidone does not substantially inhibit the metabolism of drugs metabolized by the following cytochrome P450 isozymes: CYP1A1, CYP1A2, CYP2A6, CYP2B6, CYP2C8, CYP2C9, or CYP2E1. Furthermore, in vitro studies in human liver microsomes showed that iloperidone does not have enzyme inducing properties, specifically for the following cytochrome P450 isozymes: CYP1A2, CYP2C8, CYP2C9, CYP2C19, CYP3A4 and CYP3A5.

Transporter Interaction: Iloperidone and P88 are not substrates of P-gp and iloperidone is a weak P-gp inhibitor.

12.5 Pharmacogenomics

CYP2D6 Poor Metabolizer (PM): The gene encoding CYP2D6 has polymorphisms that impact protein function. CYP2D6 poor metabolizers are individuals with two non-functioning alleles, resulting in no enzyme activity.

Pharmacokinetic data from CYP2D6 poor metabolizers (n=8) treated with iloperidone demonstrated an increase in the AUC of iloperidone and its metabolite P88 by 47% and 85%, respectively and decrease the AUC of metabolite P95 by 85% compared to normal metabolizers (n=18) [see Dosage and Administration (2.2)].

Approximately 7% of White populations, 2% of Asian populations, and 2% of African-American populations are poor metabolizers.

13 NONCLINICAL TOXICOLOGY

13.1 Carcinogenesis, Mutagenesis, Impairment of Fertility

Carcinogenesis: Lifetime carcinogenicity studies were conducted in CD-1 mice and Sprague Dawley rats. Iloperidone was administered orally at doses of 2.5, 5.0, and 10 mg/kg/day to CD-1 mice and 4, 8, and 16 mg/kg/day to Sprague Dawley rats (0.5, 1.0, and 2.0 times and 1.6, 3.2, and 6.5 times, respectively, the MRHD of 24 mg/day on a mg/m^2 basis). There was an increased incidence of malignant mammary gland tumors in female mice treated with the lowest dose (2.5 mg/kg/day) only. There were no treatment-related increases in neoplasia in rats.

The carcinogenic potential of the iloperidone metabolite P95, which is a major circulating metabolite of iloperidone in humans but is not present at significant amounts in mice or rats, was assessed in a lifetime carcinogenicity study in Wistar rats at oral doses of 25, 75, and 200 mg/kg/day in males and 50, 150, and 250 (reduced from 400) mg/kg/day in females. Drug-related neoplastic changes occurred in males, in the pituitary gland (pars distalis adenoma) at all doses and in the pancreas (islet cell adenoma) at the high dose. Plasma levels of P95 (AUC) in males at the tested doses (25, 75, and 200 mg/kg/day) were approximately 0.4, 3, and 23 times, respectively, the human exposure to P95 at the MRHD of iloperidone.

Mutagenesis: Iloperidone was negative in the Ames test and in the in vivo mouse bone marrow and rat liver micronucleus tests. Iloperidone induced chromosomal aberrations in Chinese Hamster Ovary (CHO) cells in vitro at concentrations which also caused some cytotoxicity.

The iloperidone metabolite P95 was negative in the Ames test, the V79 chromosome aberration test, and an in vivo mouse bone marrow micronucleus test.

Impairment of Fertility: Iloperidone decreased fertility at 12 and 36 mg/kg in a study in which both male and female rats were treated. The no-effect dose was 4 mg/kg, which is 1.6 times the MRHD of 24 mg/day on a mg/m^2 basis.

14 CLINICAL STUDIES

14.1 Schizophrenia

The efficacy of FANAPT in the treatment of schizophrenia was supported by 2 placebo- and active-controlled short-term (4- and 6-week) trials and one long-term placebo-controlled randomized withdrawal trial. All trials enrolled patients who met the DSM-III/IV criteria for schizophrenia.

Three instruments were used for assessing psychiatric signs and symptoms in these studies. The Positive and Negative Syndrome Scale (PANSS) and Brief Psychiatric Rating Scale (BPRS) are both multi-item inventories of general psychopathology usually used to evaluate the effects of drug treatment in schizophrenia. The Clinical Global Impression (CGI) assessment reflects the impression of a skilled observer, fully familiar with the manifestations of schizophrenia, about the overall clinical state of the patient.

Study 1, a 6-week, placebo-controlled trial (n=706), involved 2 flexible dose ranges of FANAPT (12 mg to 16 mg/day or 20 mg to 24 mg/day) compared to placebo and an active control (risperidone). For the 12 mg to 16 mg/day group, the titration schedule of FANAPT was 1 mg twice daily on Days 1 and 2, 2 mg twice daily on Days 3 and 4, 4 mg twice daily on Days 5 and 6, and 6 mg twice daily on Day 7. For the 20 mg to 24 mg/day group, the titration schedule of FANAPT was 1 mg twice daily on Day 1, 2 mg twice daily on Day 2, 4 mg twice daily on Day 3, 6 mg twice daily on Days 4 and 5, 8 mg twice daily on Day 6, and 10 mg twice daily on Day 7. The primary endpoint was change from baseline on the BPRS total score at the end of treatment (Day 42). Both the 12 mg to 16 mg/day and the 20 mg to 24 mg/day dose ranges of FANAPT were superior to placebo on the BPRS total score. The active control antipsychotic drug appeared to be superior to FANAPT in this trial within the first 2 weeks, a finding that may in part be explained by the more rapid titration that was possible for that drug. In patients in this study who remained on treatment for at least 2 weeks, iloperidone appeared to have had comparable efficacy to the active control.

Study 2 (NCT00254202), a 4-week, placebo-controlled trial (n=604), involved one fixed-dose of FANAPT (24 mg/day) compared to placebo and an active control (ziprasidone). The titration schedule for this study was similar to that for the 6-week study. This study involved titration of FANAPT starting at 1 mg twice daily on Day 1 and increasing to 2, 4, 6, 8, 10, and 12 mg twice daily on Days 2, 3, 4, 5, 6, and 7. The primary endpoint was change from baseline on the PANSS total score at the end of treatment (Day 28). The 24 mg/day FANAPT dose was superior to placebo in the PANSS total score. FANAPT appeared to have similar efficacy to the active control drug which also needed a slow titration to the target dose.

In a longer-term trial (Study 3; NCT01291511), clinically stable adult outpatients (n=303) meeting DSM-IV criteria for schizophrenia who remained stable following 12 weeks of open-label treatment with flexible doses of FANAPT (8 mg to 24 mg/day administered as twice daily doses) were randomized to placebo or to continue on their current FANAPT dose (8 mg to 24 mg/day administered as twice daily doses) for observation for possible relapse during the double-blind relapse prevention phase. Stabilization during the open-label phase was defined as being on an established dose of FANAPT that was unchanged due to efficacy in the 4 weeks prior to randomization, having CGI-Severity score of ≤4 and PANSS total score ≤70, a score of ≤4 on each of the following individual PANSS items (P1-delusions, P2-conceptual disorganization, P3-hallucinatory behavior, P6-suspiciousness/persecution, P7-hostility, or G8-uncooperativeness), and no hospitalization or increase in level of care to treat exacerbations. Relapse or impending relapse during the double-blind relapse prevention phase was defined as any of the following: hospitalization due to worsening of schizophrenia, increase (worsening) of the PANSS total score ≥30%, CGI-Improvement score ≥6, patient had suicidal, homicidal, or aggressive behavior, or need for any other antipsychotic medication.

Figure 2: Kaplan Meier Estimation of Percent Relapse/Impending Relapse (Study 3)

Based on the interim analysis, an independent data monitoring committee decided the study should be discontinued early due to evidence of efficacy. Based on results from the interim analysis, which were confirmed by the final analysis dataset, patients treated with FANAPT experienced a statistically significant longer time to relapse or impending relapse than patients who received placebo. Figure 2 displays the estimated cumulative proportion of patients with relapse or impending relapse based on the final data set.

14.2 Manic or Mixed Episodes Associated with Bipolar I Disorder

The efficacy of FANAPT in the acute treatment of manic or mixed episodes associated with bipolar I disorder in adults was supported by one multicenter, randomized, double-blind, placebo-controlled study that enrolled patients who met the DSM-5 criteria for bipolar I disorder, manic or mixed type (Study 1; NCT04819776). Demographic and baseline characteristics were similar for the FANAPT and placebo groups. Median age was 46 (range 18 to 65). 45% were female, 64% were White, and 28% were Black or African-American.

Manic symptoms were assessed with the Young Mania Rating Scale (YMRS). The YMRS is an 11-item clinician rated scale traditionally used to assess the degree of manic symptomatology. YMRS total scores may range from 0 to 60 with a higher score reflecting greater severity.

A 4-week, placebo-controlled trial (n=392) involved one fixed-dose of FANAPT (24 mg/day) compared to placebo. The primary endpoint was change in YMRS total score from baseline to Day 28. The 24 mg/day dose of FANAPT was superior to placebo on the primary endpoint. Examination of subgroups did not reveal clear evidence of differential responsiveness on the basis of age, sex, or race.

The results of the study are shown in Table 8. The LS mean changes from baseline in YMRS total score are shown in Figure 3.

Table 8: Primary Efficacy Results for Change from Baseline in YMRS Total Score in the Acute Treatment of Manic or Mixed Episodes Associated with Bipolar I Disorder in Adults (Study 1)

Study Number | Treatment Group (# ITT patients) | Primary Efficacy Endpoint: Change from Baseline to Day 28 in YMRS Total Score
 |  | Mean Baseline Score (SD) | LS Mean Change from Baseline (SE) | Placebo-substracted Differencea (95% CI)
1 | FANAPT (24 mg/day)* (n=198) | 29.2 (5.27) | -14.0 (0.64) | -4.0 (-5.70, -2.25)
 | Placebo (n=194) | 28.8 (4.64) | -10.0 (0.63)
ITT = intent-to-treat,YMRS = Young Mania Rating Scale, LS mean = Least Squares mean, SD = standard deviation, SE = standard error
aDifference (drug minus placebo) in least-squares mean change from baseline
*Dose was superior to placebo

Figure 3: Change from Baseline in YMRS Total Score by Study Visit (Study 1)

16 HOW SUPPLIED/STORAGE AND HANDLING

FANAPT tablets are white, round and identified with a logo “” debossed on one side and tablet strength “1”, “2”, “4”, “6”, “8”, “10”, or “12” debossed on the other side. Tablets are supplied in the following strengths and package configurations:

Package Configuration | Tablet Strength (mg) | NDC Code
Bottles of 60 | 1 mg | 43068-101-02
Bottles of 60 | 2 mg | 43068-102-02
Bottles of 60 | 4 mg | 43068-104-02
Bottles of 60 | 6 mg | 43068-106-02
Bottles of 60 | 8 mg | 43068-108-02
Bottles of 60 | 10 mg | 43068-110-02
Bottles of 60 | 12 mg | 43068-112-02
Titration Pack A | 2x1 mg, 2x2 mg, 2x4 mg, 2x6 mg (Total of 8 tablets) | 43068-113-04
Titration Pack B | 6x1 mg, 2x2 mg, 2x6 mg, 2x8 mg (Total of 12 tablets) | 43068-115-04
Titration Pack C | 4x1 mg, 2x2 mg, 2x6 mg (Total of 8 tablets) | 43068-114-03

Storage

Store FANAPT tablets at controlled room temperature, 25℃ (77℉); excursions permitted to 15° to 30 ℃ (59° to 86℉) [See USP Controlled Room Temperature]. Protect FANAPT tablets from exposure to light and moisture.

17 PATIENT COUNSELING INFORMATION

QT Interval Prolongation

Patients should be advised to consult their healthcare provider immediately if they feel faint, lose consciousness or have heart palpitations. Patients should be counseled not to take FANAPT with other drugs that cause QT interval prolongation [see Warnings and Precautions (5.3)]. Patients should be told to inform their healthcare provider that they are taking FANAPT before any new drug is taken.

Neuroleptic Malignant Syndrome (NMS)

Counsel patients and caregivers about a potentially fatal adverse reaction, NMS, that has been reported with administration of antipsychotic drugs, including FANAPT. Advise patients and caregivers to contact the healthcare provider or to report to the emergency room if they experience signs and symptoms of NMS [see Warnings and Precautions (5.4)].

Tardive Dyskinesia

Counsel patients on the signs and symptoms of tardive dyskinesia and to contact their healthcare provider if these abnormal movements occur [see Warnings and Precautions (5.5)].

Metabolic Changes

Educate patients of metabolic changes, how to recognize symptoms of hyperglycemia and diabetes mellitus, and the need for specific monitoring, including blood glucose, lipids, and weight. Patients should be counseled that weight gain has occurred during treatment with FANAPT [see Warnings and Precautions (5.6)].

Orthostatic Hypotension and Syncope

Educate patients about the risk of orthostatic hypotension and syncope, particularly at the time of initiating treatment, re-initiating treatment, or increasing the dose [see Warnings and Precautions (5.7)].

Leukopenia/Neutropenia

Advise patients with a pre-existing low WBC or a history of drug induced leukopenia/neutropenia that they should have their CBC monitored while taking FANAPT [see Warnings and Precautions (5.10)].

Heat Exposure and Dehydration

Educate patients regarding appropriate care in avoiding overheating and dehydration [see Warnings and Precautions (5.12)].

Interference with Cognitive and Motor Performance

Caution patients about performing activities requiring mental alertness, such as operating hazardous machinery or operating a motor vehicle, until they are reasonably certain that FANAPT therapy does not affect them adversely [see (Warnings and Precautions (5.15)].

Intraoperative Floppy Iris Syndrome

Instruct patients to tell their ophthalmologist about their use of FANAPT before cataract surgery or other procedures involving the eyes, even if the patient is no longer taking FANAPT [see Warnings and Precautions (5.16)].

Pregnancy

Advise patients that third trimester use of FANAPT may cause extrapyramidal and/or withdrawal symptoms in a neonate. Advise patients to notify their healthcare provider with known or suspected pregnancy [see Use in Specific Populations (8.1)].

Pregnancy Registry

Advise patients that there is a pregnancy exposure registry that monitors pregnancy outcomes in women exposed to FANAPT during pregnancy [see Use in Specific Populations (8.1)].

Lactation

Advise women not to breastfeed during treatment with FANAPT [see Use in Specific Populations (8.2)].

Concomitant Medication

Advise patients to inform their healthcare provider if they are taking, or plan to take, any prescription or over-the-counter drugs, since there is a potential for interactions [see Drug Interactions (7)].

Alcohol

Patients should be advised to avoid alcohol while taking FANAPT.

Distributed by:

Vanda Pharmaceuticals Inc.

Washington, D.C. 20037 USA

Vanda and Fanapt® are registered trademarks of Vanda Pharmaceuticals Inc. in the United States and other countries.